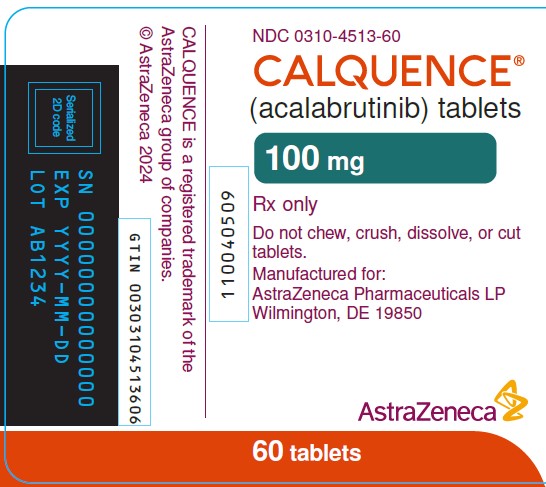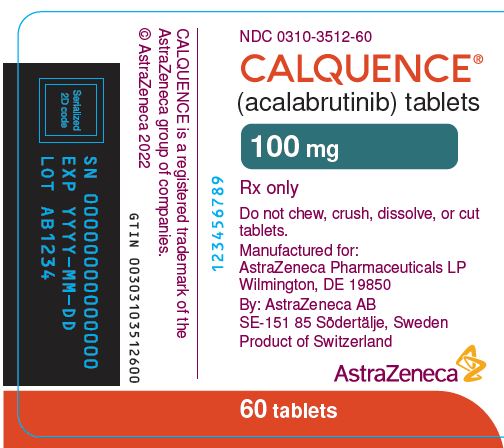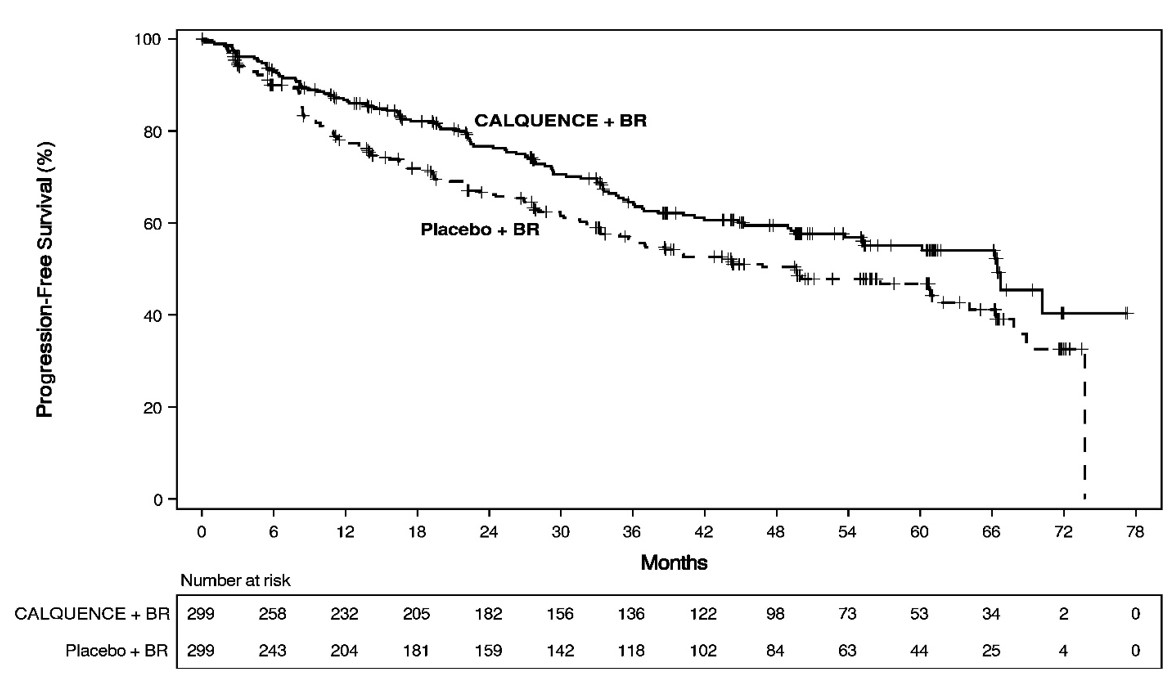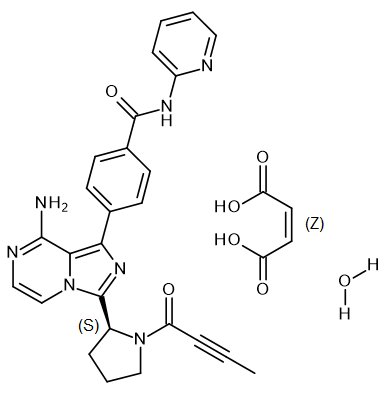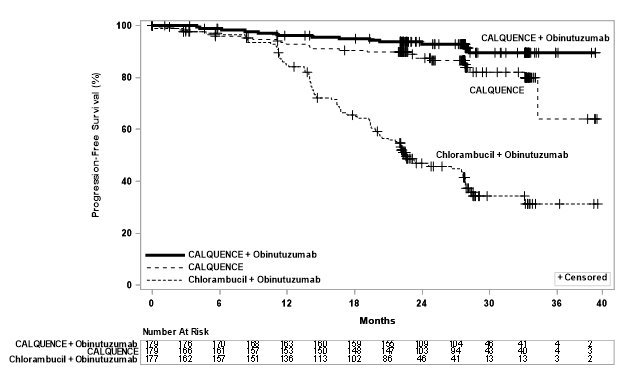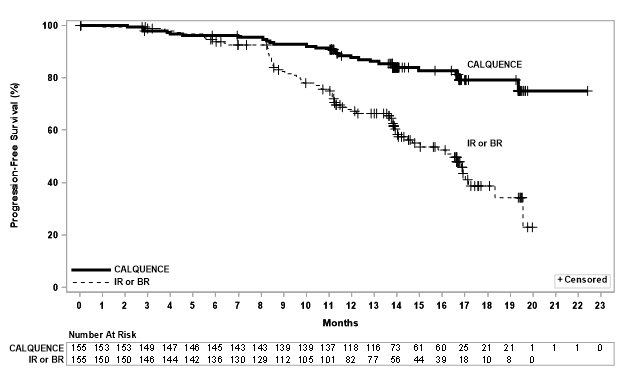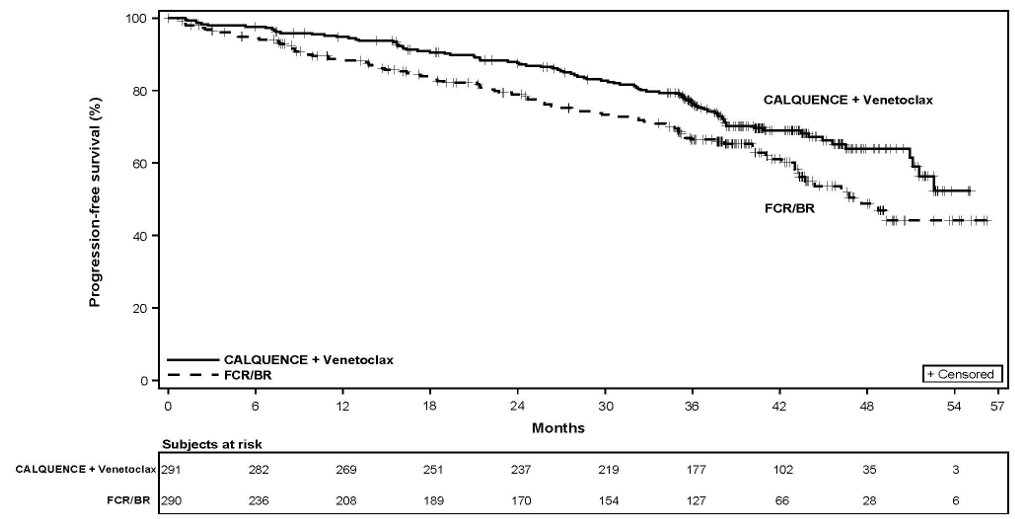 DRUG LABEL: CALQUENCE
NDC: 0310-3512 | Form: TABLET, FILM COATED
Manufacturer: AstraZeneca Pharmaceuticals LP
Category: prescription | Type: HUMAN PRESCRIPTION DRUG LABEL
Date: 20260219

ACTIVE INGREDIENTS: ACALABRUTINIB 100 mg/1 1
INACTIVE INGREDIENTS: COPOVIDONE K25-31; FERRIC OXIDE RED; FERRIC OXIDE YELLOW; HYPROMELLOSE, UNSPECIFIED; LOW-SUBSTITUTED HYDROXYPROPYL CELLULOSE, UNSPECIFIED; MANNITOL; MEDIUM-CHAIN TRIGLYCERIDES; MICROCRYSTALLINE CELLULOSE; POLYETHYLENE GLYCOL 3350; SODIUM STEARYL FUMARATE; TITANIUM DIOXIDE; WATER

HIGHLIGHTS OF PRESCRIBING INFORMATION

These highlights do not include all the information needed to use CALQUENCE safely and effectively. See full prescribing information for CALQUENCE.
CALQUENCE® (acalabrutinib) tablets, for oral use
Initial U.S. Approval: 2017

RECENT MAJOR CHANGES

Dosage and Administration, Recommended Dosage (2.1) 2/2026

Dosage and Administration, Dosage Modifications for Adverse Reactions (2.3) 2/2026

Warnings and Precautions, Serious and Opportunistic Infections (5.1) 2/2026

1 INDICATIONS AND USAGE

CALQUENCE is a kinase inhibitor indicated:

- In combination with bendamustine and rituximab for the treatment of adult patients with previously untreated mantle cell lymphoma (MCL) who are ineligible for autologous hematopoietic stem cell transplantation (HSCT). (1.1)
- For the treatment of adult patients with MCL who have received at least one prior therapy. (1.2)
- For the treatment of adult patients with chronic lymphocytic leukemia (CLL) or small lymphocytic lymphoma (SLL). (1.3)

2 DOSAGE AND ADMINISTRATION

- Recommended dose is 100 mg orally approximately every 12 hours; swallow whole with water and with or without food. (2.1)
- Advise patients not to chew, crush, dissolve, or cut tablets. (2.1)
- Manage toxicities using treatment interruption, dose reduction, or discontinuation. (2.3)
- Avoid CALQUENCE in patients with severe hepatic impairment. (8.6)

3 DOSAGE FORMS AND STRENGTHS

Tablets: 100 mg. (3)

4 CONTRAINDICATIONS

None. (4)

5 WARNINGS AND PRECAUTIONS

- Serious and Opportunistic Infections: Monitor for signs and symptoms of infection and treat promptly. (5.1)
- Hemorrhage: Monitor for bleeding and manage appropriately. (5.2)
- Cytopenias: Monitor complete blood counts regularly. (5.3)
- Second Primary Malignancies: Other malignancies have occurred, including skin cancers and other solid tumors. Advise patients to use sun protection. (5.4)
- Cardiac Arrhythmias: Monitor for symptoms of arrhythmias and manage. (5.5)
- Hepatotoxicity, Including Drug Induced Liver Injury: Monitor hepatic function throughout treatment. (5.6)

6 ADVERSE REACTIONS

The most common adverse reactions (≥ 30%), excluding laboratory abnormalities, are upper respiratory tract infection, diarrhea, headache, and musculoskeletal pain. The most common Grade 3 or 4 laboratory abnormalities (≥ 10%) are absolute neutrophil count decreased, uric acid increased, absolute lymphocyte count decreased, and platelets decreased. (6.1)

To report SUSPECTED ADVERSE REACTIONS, contact AstraZeneca at 1-800-236-9933 or FDA at 1-800-FDA-1088 or www.fda.gov/medwatch.

7 DRUG INTERACTIONS

- Strong CYP3A Inhibitors: Avoid co-administration with CALQUENCE. (2.2, 7)
- Moderate CYP3A Inhibitors: Reduce the dosage of CALQUENCE. (2.2, 7)
- Strong CYP3A Inducers: Avoid co-administration with CALQUENCE. If co-administration is unavoidable, increase the dosage of CALQUENCE. (2.2, 7)

8 USE IN SPECIFIC POPULATIONS

- Pregnancy: May cause fetal harm and dystocia. (8.1)
- Lactation: Advise not to breastfeed. (8.2)
- Severe Hepatic Impairment: Avoid use of CALQUENCE. (8.6)

FULL PRESCRIBING INFORMATION

1 INDICATIONS AND USAGE

1.1 Previously Untreated Mantle Cell Lymphoma

CALQUENCE in combination with bendamustine and rituximab is indicated for the treatment of adult patients with previously untreated mantle cell lymphoma (MCL) who are ineligible for autologous hematopoietic stem cell transplantation (HSCT).

1.2 Previously Treated Mantle Cell Lymphoma

CALQUENCE is indicated for the treatment of adult patients with MCL who have received at least one prior therapy.

1.3 Chronic Lymphocytic Leukemia or Small Lymphocytic Lymphoma

CALQUENCE is indicated for the treatment of adult patients with chronic lymphocytic leukemia (CLL) or small lymphocytic lymphoma (SLL).

2 DOSAGE AND ADMINISTRATION

2.1 Recommended Dosage

CALQUENCE Administration Instructions

Advise patients to swallow tablet whole with water. Advise patients not to chew, crush, dissolve, or cut the tablets. CALQUENCE may be taken with or without food. If a dose of CALQUENCE is missed by more than 3 hours, it should be skipped, and the next dose should be taken at its regularly scheduled time. Extra tablets of CALQUENCE should not be taken to make up for a missed dose.

CALQUENCE as Monotherapy

For patients with MCL, CLL or SLL, the recommended dosage of CALQUENCE is 100 mg taken orally approximately every 12 hours until disease progression or unacceptable toxicity.

CALQUENCE in Combination with Bendamustine and Rituximab

For patients with previously untreated MCL, the recommended dosage of CALQUENCE is 100 mg taken orally approximately every 12 hours until disease progression or unacceptable toxicity.

Start CALQUENCE on Day 1 of Cycle 1 (each cycle is 28 days) and administer until disease progression or unacceptable toxicity. Administer bendamustine 90 mg/m^2 on Days 1 and 2 and rituximab 375 mg/m^2 on Day 1 of Cycle 1 and continue for a total of 6 cycles. Patients achieving a response (PR or CR) after the first 6 cycles may receive maintenance rituximab on Day 1 of every other cycle for a maximum of 12 additional doses, starting on Cycle 8 up to Cycle 30 [see Clinical Studies (14.1)].

CALQUENCE in Combination with Obinutuzumab

For patients with previously untreated CLL or SLL, the recommended dosage of CALQUENCE is 100 mg taken orally approximately every 12 hours until disease progression or unacceptable toxicity. Start CALQUENCE at Cycle 1 (each cycle is 28 days). Start obinutuzumab at Cycle 2 for a total of 6 cycles and refer to the obinutuzumab prescribing information for recommended dosing. Administer CALQUENCE prior to obinutuzumab when given on the same day.

CALQUENCE in Combination with Venetoclax

For patients with previously untreated CLL or SLL, the recommended dosage of CALQUENCE is 100 mg taken orally approximately every 12 hours until disease progression, unacceptable toxicity or completion of 14 cycles of treatment. Start CALQUENCE at Cycle 1 (each cycle is 28 days). Start venetoclax at Cycle 3 for total of 12 cycles. Start venetoclax at 20 mg daily for first week of treatment and increase weekly as per dosing schedule for 5-week ramp up (up to 400 mg daily) as described in the venetoclax USPI. Refer to the venetoclax USPI for additional details.

2.2 Recommended Dosage for Drug Interactions

Dosage Modifications for Use with CYP3A Inhibitors or Inducers

These are described in Table 1 [see Drug Interactions (7)].

Table 1: Recommended Dosage Modifications for Use with CYP3A Inhibitors or Inducers
CYP3A | Co-administered Drug | Recommended CALQUENCE use
Inhibition | Strong CYP3A inhibitor | Avoid co-administration.; If these inhibitors will be used short-term (such as anti‑infectives for up to seven days), interrupt CALQUENCE.; After discontinuation of strong CYP3A inhibitor for at least 24 hours, resume previous dosage of CALQUENCE.
Inhibition | Moderate CYP3A inhibitor | Reduce the CALQUENCE 100 mg every 12 hours dosage to 100 mg once daily.
Induction | Strong CYP3A inducer | Avoid co-administration.; If co-administration is unavoidable, increase CALQUENCE dosage to 200 mg approximately every 12 hours.

2.3 Dosage Modifications for Adverse Reactions

Recommended dosage modifications are provided in Table 2, 3 and 4.

Table 2: Recommended Dosage Modifications for Adverse Reactions in Patients Receiving CALQUENCE Monotherapy and CALQUENCE in Combination with Obinutuzumab
Event | Adverse Reaction Occurrence | Dosage Modification (Starting dose = 100 mg approximately every 12 hours)
Grade 3 or greater non-hematologic toxicities,; Grade 3 thrombocytopenia with bleeding,; Grade 4 thrombocytopenia or; Grade 4 neutropenia lasting longer than 7 days | First and Second | Interrupt CALQUENCE.; Once toxicity has resolved to Grade 1 or baseline level, CALQUENCE may be resumed at 100 mg approximately every 12 hours.
Grade 3 or greater non-hematologic toxicities,; Grade 3 thrombocytopenia with bleeding,; Grade 4 thrombocytopenia or; Grade 4 neutropenia lasting longer than 7 days | Third | Interrupt CALQUENCE.; Once toxicity has resolved to Grade 1 or baseline level, CALQUENCE may be resumed at a reduced frequency of 100 mg once daily.
Grade 3 or greater non-hematologic toxicities,; Grade 3 thrombocytopenia with bleeding,; Grade 4 thrombocytopenia or; Grade 4 neutropenia lasting longer than 7 days | Fourth | Discontinue CALQUENCE.
Adverse reactions graded by the National Cancer Institute Common Terminology Criteria for Adverse Events (NCI CTCAE).

Table 3: Recommended Dosage Modifications for Adverse Reactions in Patients Receiving CALQUENCE in Combination with BR
Adverse Reaction | Severitya | Dosage Modification; (Starting dosage of CALQUENCE = 100 mg approximately every 12 hours)
Neutropeniab [see Warnings and Precautions (5.3)] | Absolute neutrophil count less than 0.5 x 10^9/L for greater than 7 days | Interrupt CALQUENCE. Once toxicity has resolved to Grade ≤ 2, resume CALQUENCE at starting dosage.; Upon 2nd or 3rd occurrence, reduce dosage of CALQUENCE to 100 mg once daily.c; Discontinue CALQUENCE at 4th occurrence.; For bendamustineb:; Interrupt bendamustine. Once toxicity has resolved to Grade ≤ 2, resume bendamustine and consider dosage reduction to 70 mg/m2.d,e
Thrombocytopeniaf [see Warnings and Precautions (5.3)] | Platelet count 25 to 50 x 10^9/L with clinically significant bleeding or platelet count less than 25 x 10^9/L | Interrupt CALQUENCE. Once toxicity has resolved to Grade ≤ 2 or baseline, resume CALQUENCE at starting dosage.; If recurrence, reduce dosage of CALQUENCE to 100 mg once daily.c; Consider discontinuing CALQUENCE at 3rd occurrence.; For bendamustinef:; Interrupt bendamustine. Once toxicity has resolved to Grade ≤ 2 or baseline, resume bendamustine and consider dose reduction to 70 mg/m2.e
Non-hematologic adverse reactions [see Warnings and Precautions (5)] | Grade 3 or higher | Interrupt CALQUENCE. Once toxicity has resolved to Grade ≤ 2 or baseline, resume CALQUENCE at starting dosage.; If recurrence, reduce dosage of CALQUENCE to 100 mg once daily.c; Discontinue CALQUENCE at 3rd occurrence of Grade 4 toxicity. For Grade 3 toxicity, consider the risks and benefits of continuing CALQUENCE.; For bendamustine:; Interrupt bendamustine. Once toxicity has resolved to Grade ≤ 2 or baseline, resume bendamustine and consider dose reduction to 70 mg/m2.e
a Graded per National Cancer Institute Common Terminology Criteria for Adverse Events (NCI CTCAE) version 4.03.
b For neutropenia with ANC less than 1 x 10^9/L, consideration for bendamustine dose interruption and dosage reduction to 70 mg/m^2 may be appropriate in certain circumstances.
c Dose may be re-escalated at the discretion of the physician if patient tolerates a reduced dose for ≥4 weeks.
d Consider use of myeloid growth factors before bendamustine dosage reduction.
e Consider discontinuing bendamustine if additional dosage reduction is required.
f For thrombocytopenia, a platelet count below 50 x 10^9/L should prompt bendamustine dose interruption even in the absence of clinically significant bleeding.

Table 4: Recommended Dosage Modifications for Adverse Reactions in Patients Receiving CALQUENCE in Combination with Venetoclax
Adverse Reactiona | Adverse Reaction Occurrence | Dose Modification
Grade 3 or 4 neutropenia with or without fever and/or infection; Grade 4 neutropenia lasting more than 7 days | First occurrence | Interrupt CALQUENCE and/or venetoclax.b; Once toxicity resolves to Grade ≤ 1 or baseline, restart CALQUENCE and/or venetoclax at same dose.
Grade 3 or 4 neutropenia with or without fever and/or infection; Grade 4 neutropenia lasting more than 7 days | Second occurrence | Interrupt CALQUENCE and/or venetoclax.b; Once toxicity resolves to Grade ≤ 1 or baseline, restart CALQUENCE at same dose and venetoclax at one lower dose levelc.
Grade 3 or 4 neutropenia with or without fever and/or infection; Grade 4 neutropenia lasting more than 7 days | Subsequent occurrence | Withhold CALQUENCE and/or venetoclax until toxicity resolves to Grade ≤ 1 or baseline.b,d
Grade 3 or 4 thrombocytopenia and/or bleedingf | First occurrence | Interrupt CALQUENCE and/or venetoclax. When bleeding resolves and thrombocytopenia is Grade ≤ 1 or baseline without transfusion support for 5 consecutive days, restart CALQUENCE and/or venetoclax at same dose.
Grade 3 or 4 thrombocytopenia and/or bleedingf | Second occurrence | Interrupt CALQUENCE and venetoclax until resolution of bleeding and thrombocytopenia resolves to Grade ≤ 1 or baseline.; Restart CALQUENCE at same dose and/or restart venetoclax at one lower dose level.e
Grade 3 or 4 thrombocytopenia and/or bleedingf | Subsequent occurrences of severe thrombocytopenia | Interrupt CALQUENCE and venetoclax until resolution of bleeding and thrombocytopenia resolves to Grade ≤ 1 or baseline.; Restart CALQUENCE at a reduced frequency of 100 mg once daily and/or venetoclax at one lower dose level.c,d,e
Grade 3 or 4 tumour lysis syndrome (TLS) | First and subsequent episodes | If a subject experiences blood chemistry changes suggestive of TLS, the following day’s venetoclax and acalabrutinib dose should be withheld. If resolved within 24–48 hours of last dose, treatment can be resumed at the same dose.; For events of clinical TLS or blood chemistry changes requiring more than 48 hours to resolve, venetoclax should be resumed at one lower dose level.c When resuming treatment after interruption due to TLS, monitor for TLS and provide prophylaxis.
Grade 3 other non-hematologic eventsg | First occurrence | Interrupt CALQUENCE and/or venetoclax until toxicity resolves to Grade ≤ 1.; Restart CALQUENCE and/or venetoclax at same dose.
Grade 3 other non-hematologic eventsg | Second occurrence | Interrupt CALQUENCE and/or venetoclax until toxicity resolves to Grade ≤ 1d.
Grade 4 other non-hematologic eventsg | First occurrence | Interrupt CALQUENCE and/or venetoclax until toxicity resolves to Grade ≤ 1. Restart CALQUENCE at a reduced frequency of 100 mg once daily and/or venetoclax at one lower dose level.c, e
Grade 4 other non-hematologic eventsg | Second occurrence | Interrupt CALQUENCE and/or venetoclax until toxicity resolves to Grade ≤ 1d.
a Adverse reactions graded by the National Cancer Institute Common Terminology Criteria for Adverse Events (NCI CTCAE) version 5.0.
b Growth factor may be used at physician discretion.
c See venetoclax USPI for dose level reductions details.
d Clinical judgment of the treating physician should guide the management plan of each patient based on the individual benefit/risk assessment for treatment with CALQUENCE in combination with venetoclax.
e CALQUENCE dose may be re-escalated at the discretion of the physician if patient tolerates a reduced dose for ≥4 weeks.
f Platelets may be used at physician discretion.
g Certain treatment-emergent non-hematologic AEs (e.g., venous thromboembolic events) may be managed and become clinically stable following medical intervention but may not improve to Grade ≤ 1 according to the NCI CTCAE definitions. In such cases, if a subject is clinically stable, resumption of CALQUENCE may be possible based on clinical judgement of the treating physician.

Refer to the prescribing information of each of the products used in combination with CALQUENCE for additional information for management of toxicities.

3 DOSAGE FORMS AND STRENGTHS

Tablets:100 mg acalabrutinib, orange, oval, film-coated, biconvex, debossed with ‘ACA 100’ on one side and plain on the other.

4 CONTRAINDICATIONS

None.

5 WARNINGS AND PRECAUTIONS

5.1 Serious and Opportunistic Infections

Fatal and serious infections, including opportunistic infections, have occurred in patients with hematologic malignancies treated with CALQUENCE.

Serious or Grade 3 or higher infections (bacterial, viral, or fungal) occurred in 29% of 2,055 patients exposed to CALQUENCE in clinical trials, most often due to respiratory tract infections (18% of all patients, including pneumonia in 14%) [see Adverse Reactions (6.1)]. These infections predominantly occurred in the absence of Grade 3 or 4 neutropenia, with neutropenic infection reported in 8% of all patients. Opportunistic infections in recipients of CALQUENCE have included, but are not limited to, hepatitis B virus reactivation, fungal pneumonia, Pneumocystis jirovecii pneumonia, Epstein-Barr virus reactivation, cytomegalovirus, and progressive multifocal leukoencephalopathy (PML). Consider prophylaxis in patients who are at increased risk for opportunistic infections. Monitor patients for signs and symptoms of infection and treat promptly.

In an additional cohort of patients receiving CALQUENCE in combination with venetoclax with obinutuzumab (AVO) (an unapproved regimen for previously untreated CLL/SLL in AMPLIFY), serious or Grade 3 or higher infections occurred in 25% receiving AVO compared to 14% in patients receiving AV. Fatal infections occurred in 6% receiving AVO compared to 3.1% of patients receiving AV, most commonly due to COVID-19. The safety and effectiveness of AVO has not been established in patients with previously untreated CLL/SLL [see Clinical Studies (14.3)].

5.2 Hemorrhage

Fatal and serious hemorrhagic events have occurred in patients treated with CALQUENCE. Major hemorrhage (serious or Grade 3 or higher bleeding or any central nervous system bleeding) occurred in 4.7% of patients, with fatal hemorrhage occurring in 0.1% of 2,055 patients exposed to CALQUENCE in clinical trials. Bleeding events of any grade, excluding bruising and petechiae, occurred in 39% of patients [see Adverse Reactions (6.1)].

Use of antithrombotic agents concomitantly with CALQUENCE may further increase the risk of hemorrhage. In clinical trials, major hemorrhage occurred in 5% of patients taking CALQUENCE without antithrombotic agents and 3.2% of patients taking CALQUENCE with antithrombotic agents. Consider the risks and benefits of antithrombotic agents when co-administered with CALQUENCE. Monitor patients for signs of bleeding.

Consider the benefit-risk of withholding CALQUENCE for 3 to 7 days pre- and post-surgery depending upon the type of surgery and the risk of bleeding.

5.3 Cytopenias

CALQUENCE can cause Grade 3 or 4 cytopenias. Grade 3 or 4 cytopenias included absolute neutrophil count decreased (28%), absolute lymphocyte count decreased (10%), hemoglobin decreased (9%), and platelets decreased (9%) in 1,758 patients treated with CALQUENCE alone and in combination with obinutuzumab or venetoclax; Grade 4 neutropenia developed in 14% [see Adverse Reactions (6.1)].

Monitor complete blood counts regularly during treatment. Interrupt treatment, reduce the dose, or discontinue treatment as warranted [see Dosage and Administration (2.3)].

5.4 Second Primary Malignancies

Second primary malignancies, including skin cancers and other solid tumors, occurred in 16% of 2,055 patients exposed to CALQUENCE in clinical trials [see Adverse Reactions (6.1)]. The most frequent second primary malignancy was non-melanoma skin cancer, reported in 9% of patients, followed by other solid tumors in 8% (including melanoma, lung cancer, gastrointestinal cancers, and genitourinary cancers) and hematologic malignancies (1.1%). Fatal second primary malignancies occurred in 0.8% of patients. Monitor patients for the development of second cancers and advise protection from sun exposure.

5.5 Cardiac Arrhythmias

Fatal and serious cardiac arrhythmias have occurred in patients treated with CALQUENCE. Grade 3 or 4 atrial fibrillation or flutter was reported in 2.2% of 2,055 patients treated with CALQUENCE, with all grades of atrial fibrillation or flutter reported in 7% of all patients [see Adverse Reactions (6.1)]. Grade 3 or higher ventricular arrhythmia events were reported in 0.5% of patients, including fatal cases in 0.3% of all patients. The risk of arrhythmias may be increased in patients with cardiac risk factors, hypertension, previous arrhythmias, and acute infection. Monitor for symptoms of arrhythmia (e.g., palpitations, dizziness, syncope, dyspnea) and manage as appropriate.

5.6 Hepatotoxicity, Including Drug-Induced Liver Injury

Hepatotoxicity, including severe, life-threatening, and potentially fatal cases of drug-induced liver injury (DILI), has occurred in patients treated with Bruton tyrosine kinase inhibitors, including CALQUENCE.

Evaluate bilirubin and transaminases at baseline and throughout treatment with CALQUENCE. For patients who develop abnormal liver tests after CALQUENCE, monitor more frequently for liver test abnormalities and clinical signs and symptoms of hepatic toxicity. If DILI is suspected, withhold CALQUENCE. Upon confirmation of DILI, discontinue CALQUENCE.

6 ADVERSE REACTIONS

The following clinically significant adverse reactions are discussed in greater detail in other sections of the labeling:

- Serious and Opportunistic Infections [see Warnings and Precautions (5.1)]
- Hemorrhage [see Warnings and Precautions (5.2)]
- Cytopenias [see Warnings and Precautions (5.3)]
- Second Primary Malignancies [see Warnings and Precautions (5.4)]
- Cardiac Arrhythmias [see Warnings and Precautions (5.5)]
- Hepatotoxicity, including DILI [see Warnings and Precautions (5.6)]

6.1 Clinical Trials Experience

Because clinical trials are conducted under widely varying conditions, adverse reaction rates observed in the clinical trials of a drug cannot be directly compared to rates in the clinical trials of another drug and may not reflect the rates observed in practice.

The data in the Warnings and Precautions reflect exposure to CALQUENCE 100 mg approximately every 12 hours in 2,055 patients with hematologic malignancies. Treatment includes CALQUENCE monotherapy in 1258 patients in 9 trials, and CALQUENCE combinations in 797 patients in 4 trials. Among these recipients of CALQUENCE, 89% were exposed for at least 6 months and 82% were exposed for at least one year. In this pooled safety population, adverse reactions in ≥ 30% of 2,055 patients, excluding laboratory abnormalities, were upper respiratory tract infection (37%), diarrhea (36%), headache (35%), and musculoskeletal pain (32%). The most common Grade 3 or 4 laboratory abnormalities (≥ 10%) were absolute neutrophil count decreased (32%), uric acid increased (27%), absolute lymphocyte count decreased (21%) and platelets decreased (10%).

Previously Untreated Mantle Cell Lymphoma

The safety data described below reflect exposure to CALQUENCE (100 mg approximately every 12 hours, with or without BR) in patients with MCL [see Clinical Studies (14.1)].

ECHO

The safety of CALQUENCE in combination with bendamustine and rituximab (CALQUENCE plus BR) was evaluated in 297 patients with previously untreated MCL in ECHO [see Clinical Studies (14.1)]. The trial enrolled patients with previously untreated MCL, ≥ 65 years of age with no intention for transplant, total bilirubin ≤ 1.5 × ULN, AST or ALT ≤ 2.5 × ULN, and estimated creatinine clearance of > 50 mL/min. Patients received 6 cycles (as 28-day cycles) of CALQUENCE 100 mg orally twice daily (n = 297) or placebo (n = 297) in combination with bendamustine and rituximab. Patients then received CALQUENCE 100 mg orally twice daily or placebo continuously until progressive disease or unacceptable toxicity, with 12 additional dosages of rituximab every other cycle up to Cycle 30.

The median duration of treatment with CALQUENCE was 28.6 months. A total of 171 (57.6%) patients were treated with CALQUENCE for ˃ 24 months and 122 (41.1%) patients were treated for ˃ 36 months.

Serious adverse reactions occurred in 69% of patients who received CALQUENCE plus BR. Serious adverse reactions reported in ≥ 2% of patients were pneumonia (23%; includes COVID-19 pneumonia), COVID-19 (20%; includes COVID-19 pneumonia), pyrexia (6%), second primary malignancy (7%), rash (3.4%), febrile neutropenia (3.4%), atrial fibrillation (3%), sepsis (2.7%), and anemia (2.4%). Fatal adverse reactions that occurred within 30 days of the last study treatment were reported in 12% who received CALQUENCE plus BR including COVID-19 (6%; includes COVID-19 pneumonia), pneumonia (1%), sepsis (0.3%), second primary malignancy (0.7%), and pneumonitis (0.3%).

Adverse reactions led to permanent discontinuation of CALQUENCE in 43%, dosage interruptions in 74%, and dosage reductions in 10% of patients. Adverse reactions that resulted in dosage modification in > 10% included infections, cytopenias, rashes, and gastrointestinal toxicity. Adverse reactions which resulted in permanent discontinuation of CALQUENCE in ≥ 4% of patients included COVID-19 (includes COVID-19 pneumonia) and neutropenia.

Table 5 and Table 6 summarize select adverse reactions and laboratory abnormalities observed in patients treated in ECHO.

Table 5: Adverse Reactions* (≥ 15%) in Patients with Previously Untreated MCL Who Received CALQUENCE plus BR in ECHO
Body System; Adverse Reactions* | CALQUENCE plus BR; N = 297 |  | Placebo plus BR; N = 297
Body System; Adverse Reactions* | All Grades; (%) | Grade; 3 or 4 (%) | All Grades; (%) | Grade; 3 or 4 (%)
Skin and subcutaneous tissue disorders
Rasha | 47 | 12 | 31 | 3
Infections
COVID-19b | 38 | 13 | 27 | 11
Upper respiratory tract infectionc | 30 | 0.7 | 29 | 1
Pneumoniadd | 31 | 17 | 25 | 14
Gastrointestinal disorders
Diarrhea | 37 | 3 | 28 | 2.4
Vomiting | 26 | 0.7 | 14 | 1
Constipation | 25 | 1 | 25 | 0.3
General disorders
Fatigue | 37 | 3.7 | 32 | 4.4
Pyrexia | 29 | 2.4 | 24 | 1.3
Edema | 20 | 1.3 | 19 | 0
Nervous system disorders
Headache | 31 | 1.7 | 14 | 0.7
Dizziness | 18 | 1 | 17 | 0.3
Respiratory, thoracic and mediastinal disorders
Cough | 27 | 0 | 20 | 0.3
Dyspnea | 17 | 1 | 11 | 2.7
Neoplasms
Secondary primary malignancye | 19 | 7 | 15 | 7
Musculoskeletal and connective tissue disorders
Arthralgia | 18 | 0.7 | 16 | 1
Vascular disorders
Hemorrhagef | 20 | 1.7 | 11 | 3
*Excludes laboratory terms.
a Includes rash, dermatitis, and other related terms.
b Includes the following fatal adverse reactions: n=24 for COVID-19.
c Includes upper respiratory tract infection, sinusitis, pharyngitis, and related terms.
d Includes pneumonia, terms containing pneumonia, and related infections. COVID-19 pneumonia is represented under both Pneumonia and COVID-19.
e Includes terms related to malignant neoplasms including cutaneous neoplasms.
f Includes all terms containing hematoma or hemorrhage and related terms indicative of bleeding.

Clinically relevant adverse reactions in < 15% of patients receiving CALQUENCE plus BR included bruising, abdominal pain, atrial fibrillation or flutter, and tumor lysis syndrome.

Table 6: Select Laboratory Abnormalities (≥ 15%) in Patients with Previously Untreated MCL in ECHO
Laboratory Abnormality | CALQUENCE plus BRa |  | Placebo plus BRa
Laboratory Abnormality | All grade; (%) | Grade; 3 or 4 (%) | All grade; (%) | Grade; 3 or 4 (%)
Hematologic Abnormalities
Lymphocytes decreased | 98 | 87 | 97 | 89
Hemoglobin decreased | 80 | 11 | 65 | 11
Neutrophils decreased | 76 | 56 | 77 | 51
Platelets decreased | 69 | 18 | 60 | 16
Chemistry Abnormalities
AST increased | 53 | 5 | 50 | 3.4
Uric acid increased | 45 | 45 | 40 | 40
ALT increased | 44 | 7 | 41 | 2.4
Potassium increased | 40 | 2 | 38 | 2.7
Creatinine increased | 37 | 3 | 28 | 2.4
Phosphate decreased | 36 | 4.4 | 30 | 4.7
Potassium decreased | 29 | 7 | 23 | 6
Bilirubin increased | 19 | 2 | 12 | 2
a The denominator used to calculate the rate varied between 296 and 297 based on the number of patients with a baseline value and at least one post-treatment value.

Grade 4 laboratory abnormalities in > 15% of patients treated with CALQUENCE plus BR include absolute lymphocyte count decreased (26%), absolute neutrophil count decreased (36%), and uric acid increased (17%).

Previously Treated Mantle Cell Lymphoma

ACE-LY-004

The safety data described in this section reflect exposure to CALQUENCE (100 mg approximately every 12 hours) in 124 patients with previously treated MCL in Trial LY-004 [see Clinical Studies (14.2)]. The median duration of treatment with CALQUENCE was 16.6 (range: 0.1 to 26.6) months. A total of 91 (73.4%) patients were treated with CALQUENCE for ≥ 6 months and 74 (59.7%) patients were treated for ≥ 1 year.

The most common adverse reactions (≥ 20%) of any grade were anemia, thrombocytopenia, headache, neutropenia, diarrhea, fatigue, myalgia, and bruising. Grade 1 severity for the non-hematologic, most common events were as follows: headache (25%), diarrhea (16%), fatigue (20%), myalgia (15%), and bruising (19%). The most common Grade ≥ 3 non-hematological adverse reaction (reported in at least 2% of patients) was diarrhea.

Dose reductions and discontinuation due to any adverse reaction were reported in 1.6% and 6.5% of patients, respectively.

Tables 7 and 8 present the frequency category of adverse reactions observed in patients with MCL treated with CALQUENCE.

Table 7: Non-Hematologic Adverse Reactions in ≥ 5% (All Grades) of Patients with MCL in Trial LY-004
Body System; Adverse Reactions* | CALQUENCE Monotherapy; N=124
Body System; Adverse Reactions* | All Grades (%) | Grade ≥ 3 (%)
Nervous system disorders
Headache | 39 | 1.6
Gastrointestinal disorders
Diarrhea | 31 | 3.2
Nausea | 19 | 0.8
Abdominal pain | 15 | 1.6
Constipation | 15 | -
Vomiting | 13 | 1.6
General disorders
Fatigue | 28 | 0.8
Musculoskeletal and connective tissue disorders
Myalgia | 21 | 0.8
Skin and subcutaneous tissue disorders
Bruisinga | 21 | -
Rashb | 18 | 0.8
Vascular disorders
Hemorrhagec | 8 | 0.8
Respiratory, thoracic and mediastinal disorders
Epistaxis | 6 | -

*Per NCI CTCAE version 4.03.

a Bruising: Includes all terms containing ‘bruise,’ ‘contusion,’ ‘petechiae,’ or ‘ecchymosis’.

b Rash: Includes all terms containing ‘rash’.

c Hemorrhage: Includes all terms containing ‘hemorrhage’ or ‘hematoma’.

Table 8: Hematologic Adverse Reactions Reported in ≥ 20% of Patients with MCL in Trial LY-004
Hematologic; Adverse Reactions* | CALQUENCE Monotherapy; N=124
Hematologic; Adverse Reactions* | All Grades (%) | Grade ≥ 3 (%)
Hemoglobin decreased | 46 | 10
Platelets decreased | 44 | 12
Neutrophils decreased | 36 | 15

*Per NCI CTCAE version 4.03; based on laboratory measurements and adverse reactions.

Increases in creatinine to 1.5 to 3 times the upper limit of normal (ULN) occurred in 4.8% of patients.

Chronic Lymphocytic Leukemia

The safety data described below reflect exposure to CALQUENCE (100 mg approximately every 12 hours, with or without obinutuzumab) in 511 patients with CLL from two randomized controlled clinical trials [see Clinical Studies (14.3)].

The most common adverse reactions (≥ 30%) of any grade in patients with CLL were anemia, neutropenia, thrombocytopenia, headache, upper respiratory tract infection, and diarrhea.

ELEVATE-TN

The safety of CALQUENCE plus obinutuzumab (CALQUENCE+G), CALQUENCE monotherapy, and obinutuzumab plus chlorambucil (GClb) was evaluated in a randomized, multicenter, open-label, actively controlled trial in 526 patients with previously untreated CLL [see Clinical Studies (14.3)].

Patients randomized to the CALQUENCE+G arm were treated with CALQUENCE and obinutuzumab in combination for six cycles, then with CALQUENCE as monotherapy until disease progression or unacceptable toxicity. Patients initiated obinutuzumab on Day 1 of Cycle 2, continuing for a total of 6 cycles. Patient randomized to CALQUENCE monotherapy received CALQUENCE approximately every 12 hours until disease progression or unacceptable toxicity. The trial required age ≥ 65 years of age or 18 to < 65 years of age with a total Cumulative Illness Rating Scale (CIRS) > 6 or creatinine clearance of 30 to 69 mL/min, hepatic transaminases ≤ 3 times ULN and total bilirubin ≤ 1.5 times ULN, and allowed patients to receive antithrombotic agents other than warfarin or equivalent vitamin K antagonists.

During randomized treatment, the median duration of exposure to CALQUENCE in the CALQUENCE+G and CALQUENCE monotherapy arms was 27.7 months (range 0.3 to 40 months), with 95% and 92% and 89% and 86% of patients with at least 6 months and 12 months of exposure, respectively. In the obinutuzumab and chlorambucil arm the median number of cycles was 6 with 84% of patients receiving at least 6 cycles of obinutuzumab, 70% of patients received at least 6 cycles of chlorambucil. Eighty-five percent of patients in the CALQUENCE+G arm received at least 6 cycles of obinutuzumab.

In the CALQUENCE+G and CALQUENCE monotherapy arms, fatal adverse reactions that occurred in the absence of disease progression and with onset within 30 days of the last study treatment were reported in 2% for each treatment arm, most often from infection. Serious adverse reactions were reported in 39% of patients in the CALQUENCE+G arm and 32% in the CALQUENCE monotherapy arm, most often due to events of pneumonia (2.8% to 7%).

In the CALQUENCE+G arm, adverse reactions led to treatment discontinuation in 11% of patients and a dose reduction of CALQUENCE in 7% of patients. In the CALQUENCE monotherapy arm, adverse reactions led to discontinuation in 10% and dose reduction in 4% of patients.

Tables 9 and 10 present adverse reactions and laboratory abnormalities identified in the ELEVATE-TN trial.

Table 9: Common Adverse Reactions (≥ 15% Any Grade) with CALQUENCE in Patients with CLL (ELEVATE-TN)
Body System; Adverse Reaction* | CALQUENCE plus Obinutuzumab N=178 |  | CALQUENCE Monotherapy; N=179 |  | Obinutuzumab plus Chlorambucil N=169
Body System; Adverse Reaction* | All Grades (%) | Grade ≥ 3 (%) | All Grades (%) | Grade ≥ 3 (%) | All Grades (%) | Grade ≥ 3 (%)
Infections
Infection† | 69 | 22‡ | 65 | 14‡ | 46 | 13‡
Upper respiratory tract infection§ | 39 | 2.8 | 35 | 0 | 17 | 1.2
Lower respiratory tract infectiona | 24 | 8 | 18 | 4.5 | 7 | 1.8
Urinary tract infection | 15 | 1.7 | 15 | 2.8 | 5 | 0.6
Blood and lymphatic system disordersb
Neutropeniac | 53 | 37 | 23 | 13 | 78 | 50
Anemiad | 52 | 12 | 53 | 10 | 54 | 14
Thrombocytopeniae | 51 | 12 | 32 | 3.4 | 61 | 16
Lymphocytosisf | 12 | 11 | 16 | 15 | 0.6 | 0.6
Nervous system disorders
Headache | 40 | 1.1 | 39 | 1.1 | 12 | 0
Dizziness | 20 | 0 | 12 | 0 | 7 | 0
Gastrointestinal disorders
Diarrhea | 39 | 4.5 | 35 | 0.6 | 21 | 1.8
Nausea | 20 | 0 | 22 | 0 | 31 | 0
Musculoskeletal and connective tissue disorders
Musculoskeletal paing | 37 | 2.2 | 32 | 1.1 | 16 | 2.4
Arthralgia | 22 | 1.1 | 16 | 0.6 | 4.7 | 1.2
General disorders and administration site conditions
Fatigueh | 34 | 2.2 | 23 | 1.1 | 24 | 1.2
Skin and subcutaneous tissue disorders
Bruisingi | 31 | 0 | 21 | 0 | 5 | 0
Rashj | 26 | 2.2 | 25 | 0.6 | 9 | 0.6
Vascular disorders
Hemorrhagek | 20 | 1.7 | 20 | 1.7 | 6 | 0

*Per NCI CTCAE version 4.03.

† Includes any adverse reactions involving infection or febrile neutropenia.

‡ Includes 3 fatal cases in the CALQUENCE plus obinutuzumab arm, 3 fatal cases in the CALQUENCE monotherapy arm and 1 fatal case in the obinutuzumab plus chlorambucil arm.

§ Includes upper respiratory tract infection, nasopharyngitis and sinusitis.

a Includes pneumonia, lower respiratory tract infection, bronchitis, bronchiolitis, tracheitis, and lung infection.

b Derived from adverse reaction and laboratory data.

c Includes neutropenia, neutrophil count decreased, and related laboratory data.

d Includes anemia, red blood cell count decreased, and related laboratory data.

e Includes thrombocytopenia, platelet count decreased, and related laboratory data.

f Includes lymphocytosis, lymphocyte count increased, and related laboratory data.

g Includes back pain, bone pain, musculoskeletal chest pain, musculoskeletal pain, musculoskeletal discomfort, myalgia, neck pain, pain in extremity and spinal pain.

h Includes asthenia, fatigue, and lethargy.

i Includes bruise, contusion, and ecchymosis.

j Includes rash, dermatitis, and other related terms.

k Includes hemorrhage, hematoma, hemoptysis, hematuria, menorrhagia, hemarthrosis, and epistaxis.

Other clinically relevant adverse reactions (all grades incidence < 15%) in recipients of CALQUENCE (CALQUENCE in combination with obinutuzumab and monotherapy) included:

- Neoplasms: second primary malignancy (10%), non-melanoma skin cancer (5%)
- Cardiac disorders: atrial fibrillation or flutter (3.6%), hypertension (5%)
- Infection: herpesvirus infection (6%)

Table : Select Non-Hematologic Laboratory Abnormalities (≥ 15% Any Grade), New or Worsening from Baseline in Patients Receiving CALQUENCE (ELEVATE-TN)
Laboratory Abnormality [Per NCI CTCAE version 4.03] [Excludes electrolytes] | CALQUENCE plus Obinutuzumab N=178 |  | CALQUENCE Monotherapy; N=179 |  | Obinutuzumab plus Chlorambucil N=169
Laboratory Abnormality [Per NCI CTCAE version 4.03] [Excludes electrolytes] | All Grades (%) | Grade ≥ 3 (%) | All Grades (%) | Grade ≥ 3 (%) | All Grades (%) | Grade ≥ 3 (%)
Uric acid increase | 29 | 29 | 22 | 22 | 37 | 37
ALT increase | 30 | 7 | 20 | 1.1 | 36 | 6
AST increase | 38 | 5 | 17 | 0.6 | 60 | 8
Bilirubin increase | 13 | 0.6 | 15 | 0.6 | 11 | 0.6

Increases in creatinine to 1.5 to 3 times ULN occurred in 3.9% and 2.8% of patients in the CALQUENCE combination arm and monotherapy arm, respectively.

ASCEND

The safety of CALQUENCE in patients with relapsed or refractory CLL was evaluated in a randomized, open-label study (ASCEND) [see Clinical Studies (14.3)]. The trial enrolled patients with relapsed or refractory CLL after at least one prior therapy and required hepatic transaminases ≤ 2 times ULN, total bilirubin ≤ 1.5 times ULN, and an estimated creatinine clearance ≥ 30 mL/min. The trial excluded patients having an absolute neutrophil count < 500/µL, platelet count < 30,000/µL, prothrombin time or activated partial thromboplastin time > 2 times ULN, significant cardiovascular disease, or a requirement for strong CYP3A inhibitors or inducers. Patients were allowed to receive antithrombotic agents other than warfarin or equivalent vitamin K antagonist.

In ASCEND, 154 patients received CALQUENCE (100 mg approximately every 12 hours until disease progression or unacceptable toxicity), 118 received idelalisib (150 mg approximately every 12 hours until disease progression or unacceptable toxicity) with up to 8 infusions of a rituximab product, and 35 received up to 6 cycles of bendamustine and a rituximab product. The median age overall was 68 years (range: 32-90); 67% were male; 92% were white; and 88% had an ECOG performance status of 0 or 1.

In the CALQUENCE arm, serious adverse reactions occurred in 29% of patients. Serious adverse reactions in > 5% of patients who received CALQUENCE included lower respiratory tract infection (6%). Fatal adverse reactions within 30 days of the last dose of CALQUENCE occurred in 2.6% of patients, including from second primary malignancies and infection.

In recipients of CALQUENCE, permanent discontinuation due to an adverse reaction occurred in 10% of patients, most frequently due to second primary malignancies followed by infection. Adverse reactions led to dosage interruptions of CALQUENCE in 34% of patients, most often due to respiratory tract infections followed by neutropenia, and dose reduction in 3.9% of patients.

Selected adverse reactions are described in Table 11 and non-hematologic laboratory abnormalities are described in Table 12. These tables reflect exposure to CALQUENCE with median duration of 15.7 months with 94% of patients on treatment for greater than 6 months and 86% of patients on treatment for greater than 12 months. The median duration of exposure to idelalisib was 11.5 months with 72% of patients on treatment for greater than 6 months and 48% of patients on treatment for greater than 12 months. Eighty-three percent of patients completed 6 cycles of bendamustine and rituximab product.

Table 11: Common Adverse Reactions (≥ 15% Any Grade) with CALQUENCE in Patients with CLL (ASCEND)
Body System; Adverse Reaction* | CALQUENCE; N=154 |  | Idelalisib plus; Rituximab; Product N=118 |  | Bendamustine plus Rituximab Product; N=35
Body System; Adverse Reaction* | All Grades (%) | Grade ≥ 3 (%) | All Grades (%) | Grade ≥ 3 (%) | All Grades (%) | Grade ≥ 3 (%)
Infections
Infection† | 56 | 15‡ | 65 | 28‡ | 49 | 11
Upper respiratory tract infection§ | 29 | 1.9 | 26 | 3.4 | 17 | 2.9
Lower respiratory tract infection a | 23 | 6 | 26 | 15 | 14 | 6
Blood and lymphatic system disordersb
Neutropeniac | 48 | 23 | 79 | 53 | 80 | 40
Anemiad | 47 | 15 | 45 | 8 | 57 | 17
Thrombocytopeniae | 33 | 6 | 41 | 13 | 54 | 6
Lymphocytosisf | 26 | 19 | 23 | 18 | 2.9 | 2.9
Nervous system disorders
Headache | 22 | 0.6 | 6 | 0 | 0 | 0
Gastrointestinal disorders
Diarrheag | 18 | 1.3 | 49 | 25 | 14 | 0
Vascular disorders
Hemorrhageh | 16 | 1.3 | 5 | 1.7 | 6 | 2.9
General disorders
Fatiguei | 15 | 1.9 | 13 | 0.8 | 31 | 6
Musculoskeletal and connective tissue disorders
Musculoskeletal painj | 15 | 1.3 | 15 | 1.7 | 2.9 | 0

* Per NCI CTCAE version 4.03.

† Includes any adverse reactions involving infection or febrile neutropenia.

‡ Includes 1 fatal case in the CALQUENCE monotherapy arm and 1 fatal case in the Idelalisib plus Rituximab arm.

§ Includes upper respiratory tract infection, rhinitis and nasopharyngitis.

a Includes pneumonia, lower respiratory tract infection, bronchitis, bronchiolitis, tracheitis, and lung infection.

b Derived from adverse reaction and laboratory data.

c Includes neutropenia, neutrophil count decreased, and related laboratory data.

d Includes anemia, red blood cell decreased, and related laboratory data.

e Includes thrombocytopenia, platelet count decreased, and related laboratory data.

f Includes lymphocytosis, lymphocyte count increased and related laboratory data.

g Includes colitis, diarrhea, and enterocolitis.

h Includes hemorrhage, hematoma, hemoptysis, hematuria, menorrhagia, hemarthrosis, and epistaxis.

i Includes asthenia, fatigue, and lethargy.

j Includes back pain, musculoskeletal chest pain, musculoskeletal pain, musculoskeletal discomfort, pain in extremity, myalgia, spinal pain and bone pain.

Other clinically relevant adverse reactions (all grades incidence < 15%) in recipients of CALQUENCE included:

- Skin and subcutaneous disorders: bruising (10%), rash (9%)
- Neoplasms: second primary malignancy (12%), non-melanoma skin cancer (6%)
- Musculoskeletal and connective tissue disorders: arthralgia (8%)
- Cardiac disorders: atrial fibrillation or flutter (5%), hypertension (3.2%)
- Infection: herpesvirus infection (4.5%)

Table 12: Select Non-Hematologic Laboratory Abnormalities (≥ 10% Any Grade), New or Worsening from Baseline in Patients Receiving CALQUENCE (ASCEND)
Laboratory Abnormality [Excludes electrolytes] | CALQUENCE N=154 |  | Idelalisib plus Rituximab Product N=118 |  | Bendamustine plus Rituximab Product N=35
Laboratory Abnormality [Excludes electrolytes] | All Grades (%) | Grade ≥ 3 (%) | All Grades (%) | Grade ≥ 3 (%) | All Grades (%) | Grade ≥ 3 (%)
Uric acid increase | 15 | 15 | 11 | 11 | 23 | 23
ALT increase | 15 | 1.9 | 59 | 23 | 26 | 2.9
AST increase | 13 | 0.6 | 48 | 13 | 31 | 2.9
Bilirubin increase | 13 | 1.3 | 16 | 1.7 | 26 | 11
Per NCI CTCAE version 5

Increases in creatinine to 1.5 to 3 times ULN occurred in 1.3% of patients who received CALQUENCE.

AMPLIFY

The safety of CALQUENCE in patients with previously untreated CLL was evaluated in a randomized, multicenter, open-label study (AMPLIFY), in which 291 patients received CALQUENCE plus venetoclax (AV), and 259 patients received Investigator’s choice of FCR/BR (fludarabine plus cyclophosphamide plus rituximab or bendamustine plus rituximab) [see Clinical Studies (14.3)].

Among patients who received AV, 96% were exposed for 6 months or longer and 91% were exposed for greater than one year. The median duration of exposure to CALQUENCE was 12.9 months (range: 1 to 18 months) and to venetoclax was 11.1 months (range: 2 to 14 months).

Serious adverse reactions occurred in 25% of patients receiving AV. The most common serious adverse reactions (≥ 2%) were COVID-19 including COVID-19 pneumonia (9%), second primary malignancies (2.7%), and neutropenia (2.1%). Fatal adverse events occurred in 3.4% of patients. The most common fatal adverse events included COVID-19 and COVID-19 pneumonia.

Treatment discontinuation of CALQUENCE due to adverse reactions occurred in 8% of patients receiving AV. The most common adverse reaction (≥ 2%) leading to treatment discontinuation was COVID-19 pneumonia (2.1%). Dose reduction of CALQUENCE occurred in 6% of patients. Neutropenia was the only adverse reaction leading to dose reduction that occurred in ≥ 1% of patients.

Table 13 and Table 14 summarize select adverse reactions and laboratory abnormalities observed in patients treated in AMPLIFY.

Table 13: Adverse Reactions* (≥ 15% Any Grade) in Patients with Previously Untreated CLL Who Received CALQUENCE plus Venetoclax in AMPLIFY
Body System; Adverse Reactions* | CALQUENCE plus Venetoclax; N = 291 |  | Investigator’s choice of FCR or BR; N = 259
Body System; Adverse Reactions* | All Grades; (%) | Grade; 3 or 4 (%) | All Grades; (%) | Grade; 3 or 4 (%)
Nervous system disorders
Headache | 35 | 1.4 | 8 | 0.4
Gastrointestinal disorders
Diarrhea | 33 | 1.7 | 11 | 0.4
Nausea | 15 | 0 | 36 | 0
Musculoskeletal and connective tissue disorders
Musculoskeletal pain a | 25 | 0.7 | 14 | 0.8
Infections
COVID-19 | 21 | 6 | 3.9 | 1.5
General disorders
Fatigue b | 18 | 0.3 | 17 | 1.5
Skin and subcutaneous tissue disorders
Bruising c | 17 | 0 | 1.5 | 0
Rash d | 16 | 1 | 16 | 1.5
*Excludes laboratory terms.
a Includes back pain, bone pain, musculoskeletal chest pain, musculoskeletal pain, musculoskeletal discomfort, myalgia, neck pain, pain in extremity, spinal pain, non-cardiac chest pain and pain in jaw.
b Includes fatigue and asthenia.
c Includes increased tendency to bruise, contusion, and ecchymosis.
d Includes rash, dermatitis, and other related terms.

Clinically relevant adverse reactions in < 15% of patients receiving CALQUENCE plus Venetoclax included upper respiratory tract infections, lower respiratory tract infection, arthralgia, pneumonia, hemorrhage, dizziness, constipation, vomiting, second primary malignancy and hypertension.

Table 14: Laboratory Abnormalities (≥ 15% Any Grade), New or Worsening from Baseline in in Patients with Previously Untreated CLL Who Received CALQUENCE plus Venetoclax in AMPLIFY
Laboratory Abnormality | CALQUENCE plus Venetoclax a |  | Investigator’s choice of FCR or BR a
Laboratory Abnormality | All grade (%) | Grade 3 or 4 (%) | All grade (%) | Grade 3 or 4 (%)
Hematologic Abnormalities
Neutrophils decreased | 78 | 38 | 80 | 53
Lymphocytes decreased | 56 | 12 | 92 | 73
Platelets decreased | 43 | 5 | 59 | 15
Hemoglobin decreased | 35 | 7 | 56 | 8
Chemistry Abnormalities
Glucose increased | 74 | 0 | 84 | 0
Calcium decreased | 30 | 0.7 | 25 | 2.3
ALT increased | 26 | 3.1 | 28 | 1.6
Urate increased | 25 | 25 | 23 | 23
LDH increased | 24 | 0 | 40 | 0
Potassium increased | 22 | 2.4 | 12 | 3.1
AST increased | 22 | 1.4 | 28 | 1.6
ALP increased | 20 | 0 | 15 | 0
Glucose decreased | 20 | 0.3 | 5 | 0
Creatinine increased | 19 | 0.3 | 12 | 0.8
Sodium increased | 15 | 0.3 | 9 | 0.4
a The denominator used to calculate the rate varied between 256 and 290 based on the number of patients with a baseline value and at least one post-treatment value.

Grade 4 laboratory abnormalities in > 15% of patients treated with CALQUENCE plus Venetoclax include absolute neutrophil count decreased (15%).

6.2 Postmarketing Experience

The following adverse reactions have been identified during post-approval use of CALQUENCE. Because these reactions are reported voluntarily from a population of uncertain size, it is not always possible to reliably estimate their frequency or establish a causal relationship to drug exposure.

- Cardiac disorders: ventricular arrhythmias
- Hepatobiliary disorders: drug induced liver injury

7 DRUG INTERACTIONS

7.1 Effect of Other Drugs on CALQUENCE

Strong CYP3A Inhibitors
Clinical Effect | Co-administration of CALQUENCE with a strong CYP3A inhibitor increased acalabrutinib plasma concentrations [see Clinical Pharmacology (12.3)]. Increased acalabrutinib concentrations may result in increased toxicity.
Prevention or Management | Avoid co-administration of CALQUENCE with strong CYP3A inhibitors. Alternatively, if the inhibitor will be used short-term, interrupt CALQUENCE [see Dosage and Administration (2.2)].
Moderate CYP3A Inhibitors
Clinical Effect | Co-administration of CALQUENCE with a moderate CYP3A inhibitor may increase acalabrutinib plasma concentration [see Clinical Pharmacology (12.3)]. Increased acalabrutinib concentrations may result in increased toxicity.
Prevention or Management | Reduce the dosage of CALQUENCE when co-administered with a moderate CYP3A inhibitor [see Dosage and Administration (2.2)].
Strong CYP3A Inducers
Clinical Effect | Co-administration of CALQUENCE with a strong CYP3A inducer decreased acalabrutinib plasma concentration [see Clinical Pharmacology (12.3)]. Decreased acalabrutinib concentrations may reduce CALQUENCE activity.
Prevention or Management | Avoid co-administration of CALQUENCE with strong CYP3A inducers. If co-administration is unavoidable, increase the dosage of CALQUENCE [see Dosage and Administration (2.2)].

8 USE IN SPECIFIC POPULATIONS

8.1 Pregnancy

Risk Summary

Based on findings in animals, CALQUENCE may cause fetal harm and dystocia when administered to a pregnant woman. There are no available data in pregnant women to inform the drug-associated risk. In animal reproduction studies, administration of acalabrutinib to animals during organogenesis resulted in dystocia in rats and reduced fetal growth in rabbits at maternal exposures (AUC) 2 times exposures in patients at the recommended dose of 100 mg approximately every 12 hours (see Data). Advise pregnant women of the potential risk to a fetus.

The estimated background risk of major birth defects and miscarriage for the indicated population is unknown. All pregnancies have a background risk of birth defect, loss, or other adverse outcomes. In the U.S. general population, the estimated background risk of major birth defects and miscarriage in clinically recognized pregnancies is 2 to 4% and 15 to 20%, respectively.

Data

Animal Data

In a combined fertility and embryo-fetal development study in female rats, acalabrutinib was administered orally at doses up to 200 mg/kg/day starting 14 days prior to mating through gestational day [GD] 17. No effects on embryo-fetal development and survival were observed. The AUC at 200 mg/kg/day in pregnant rats was approximately 9 times the AUC in patients at the recommended dose of 100 mg approximately every 12 hours. The presence of acalabrutinib and its active metabolite were confirmed in fetal rat plasma.

In an embryo-fetal development study in rabbits, pregnant animals were administered acalabrutinib orally at doses up to 200 mg/kg/day during the period of organogenesis (from GD 6-18). Administration of acalabrutinib at doses ≥ 100 mg/kg/day produced maternal toxicity and 100 mg/kg/day resulted in decreased fetal body weights and delayed skeletal ossification. The AUC at 100 mg/kg/day in pregnant rabbits was approximately 2 times the AUC in patients at 100 mg approximately every 12 hours.

In a pre- and postnatal development study in rats, acalabrutinib was administered orally to pregnant animals during organogenesis, parturition and lactation, at doses of 50, 100, and 150 mg/kg/day. Dystocia (prolonged or difficult labor) and mortality of offspring were observed at doses ≥ 100 mg/kg/day. The AUC at 100 mg/kg/day in pregnant rats was approximately 2 times the AUC in patients at 100 mg approximately every 12 hours. Underdeveloped renal papilla was also observed in F1 generation offspring at 150 mg/kg/day with an AUC approximately 5 times the AUC in patients at 100 mg approximately every 12 hours.

8.2 Lactation

Risk Summary

No data are available regarding the presence of acalabrutinib or its active metabolite in human milk, its effects on the breastfed child, or on milk production. Acalabrutinib and its active metabolite were present in the milk of lactating rats. Due to the potential for adverse reactions in a breastfed child from CALQUENCE, advise lactating women not to breastfeed while taking CALQUENCE and for 2 weeks after the last dose.

8.3 Females and Males of Reproductive Potential

CALQUENCE may cause embryo-fetal harm and dystocia when administered to pregnant women [see Use in Specific Populations (8.1)].

Pregnancy Testing

Pregnancy testing is recommended for females of reproductive potential prior to initiating CALQUENCE therapy.

Contraception

Females

Advise female patients of reproductive potential to use effective contraception during treatment with CALQUENCE and for 1 week following the last dose of CALQUENCE. If this drug is used during pregnancy, or if the patient becomes pregnant while taking this drug, the patient should be informed of the potential hazard to a fetus.

8.4 Pediatric Use

The safety and efficacy of CALQUENCE in pediatric patients have not been established.

8.5 Geriatric Use

CLL and Previously Treated MCL

Of the 1,758 CALQUENCE-treated patients with B-cell malignancies (excluding previously untreated MCL) in clinical trials, 1,074 (61%) were 65 years of age or older, and 341 (19%) were 75 years of age or older. Among patients 65 years of age or older, 73% had Grade 3 or higher adverse reactions and 55% had serious adverse reactions. Among patients younger than age 65, 58% had Grade 3 or higher adverse reactions and 35% had serious adverse reactions. No clinically relevant differences in efficacy were observed between patients ≥ 65 years and younger.

Of patients that received CALQUENCE in combination with venetoclax in AMPLIFY, 33% (97/291) were ≥ 65 years of age, and 4.5% (13/291) were ≥ 75 years of age. In patients 65 years of age or older and younger than age 65, the fatal adverse reactions were 5% and 2.6% respectively. No clinically relevant differences in efficacy were observed between patients ≥ 65 years of age and younger adults.

Previously Untreated MCL

Of the 297 CALQUENCE-treated patients with previously untreated MCL, 214 (72%) were 65 to 74 years of age and 83 (28%) were 75 years of age and older. No clinically relevant differences in safety or efficacy were observed between patients ages 65 to 74 years and those who were 75 years of age and older.

8.6 Hepatic Impairment

Avoid use of CALQUENCE in patients with severe hepatic impairment (Child-Pugh class C). No dosage adjustment of CALQUENCE is recommended in patients with mild (Child-Pugh class A) or moderate (Child-Pugh class B) hepatic impairment. The safety of CALQUENCE has not been evaluated in patients with moderate or severe hepatic impairment [see Clinical Pharmacology (12.3)].

11 DESCRIPTION

CALQUENCE (acalabrutinib) is a kinase inhibitor. The molecular formula for acalabrutinib maleate is C26H23N7O2•C4H4O4.H2O, and the molecular weight is 599.59. The chemical name is 4-{8-Amino-3-[(2S)-1-(but-2-ynoyl) pyrrolidin-2-yl] imidazo[1,5-a]pyrazin-1-yl}-N-(pyridin-2-yl)benzamide (2Z)-2-butenedioic acid hydrate.

The chemical structure of acalabrutinib is shown below:

Acalabrutinib maleate is a white to pale brown powder with pH-dependent solubility. It is freely soluble in water at pH values below 3 and practically insoluble at pH values above 6.

CALQUENCE tablets are for oral administration. Each tablet contains 100 mg of acalabrutinib (equivalent to 129 mg of acalabrutinib maleate). Inactive ingredients in the tablet core are low-substituted hydroxypropyl cellulose, mannitol, microcrystalline cellulose, and sodium stearyl fumarate. The tablet coating consists of copovidone, ferric oxide yellow, ferric oxide red, hypromellose, medium-chain triglycerides, polyethylene glycol 3350, purified water, and titanium dioxide.

12 CLINICAL PHARMACOLOGY

12.1 Mechanism of Action

Acalabrutinib is a small-molecule inhibitor of Bruton tyrosine kinase (BTK). Acalabrutinib and its active metabolite, ACP-5862, form a covalent bond with a cysteine residue in the BTK active site, leading to inhibition of BTK enzymatic activity. BTK is a signaling molecule of the B cell antigen receptor (BCR) and cytokine receptor pathways. In B cells, BTK signaling results in activation of pathways necessary for B-cell proliferation, trafficking, chemotaxis, and adhesion. In nonclinical studies, acalabrutinib inhibited BTK‑mediated activation of downstream signaling proteins CD86 and CD69 and inhibited malignant B-cell proliferation and tumor growth in mouse xenograft models.

12.2 Pharmacodynamics

In patients with B-cell malignancies dosed with acalabrutinib 100 mg approximately every 12 hours, median steady state BTK occupancy of ≥ 95% in peripheral blood was maintained over 12 hours, resulting in inactivation of BTK throughout the recommended dosing interval.

Cardiac Electrophysiology

At a dose 4 times the approved recommended dosage, CALQUENCE does not prolong the QTc interval to any clinically relevant extent.

12.3 Pharmacokinetics

Acalabrutinib and its active metabolite, ACP-5862, exposures increase proportionally with dose across a dose range of 75 to 250 mg (0.75 to 2.5 times the approved recommended single dosage) in patients with B-cell malignancies. At the recommended dose of 100 mg twice daily, the geometric mean (% coefficient of variation [CV]) daily area under the plasma drug concentration over time curve (AUC24h) and maximum plasma concentration (Cmax) for acalabrutinib were 1843 (38%) ng•h/mL and 563 (29%) ng/mL, respectively, and for ACP-5862 were 3947 (43%) ng•h/mL and 451 (52%) ng/mL, respectively.

Absorption

The geometric mean absolute bioavailability of acalabrutinib was 25%. Median (min, max) time to peak plasma concentration (Tmax) of acalabrutinib and its active metabolite, ACP-5862 were 0.5 (0.2, 3.0) hours and 0.75 (0.5, 4.0) hours, respectively.

Effect of Food

In healthy subjects, administration of a single 100 mg dose of acalabrutinib with a high-fat, high-calorie meal (approximately 918 calories, 59 grams carbohydrate, 59 grams fat, and 39 grams protein) did not affect the mean AUC as compared to dosing under fasted conditions. Resulting Cmax decreased by 54% and Tmax was delayed 1-2 hours.

Distribution

The geometric mean (% CV) steady-state volume of distribution (Vss) of acalabrutinib and its active metabolite, ACP-5862 was approximately 101 (52%) L and 67 (32%) L, respectively. Reversible binding to human plasma protein of acalabrutinib and its active metabolite, ACP-5862, were 97.5% and 98.6%, respectively. The mean blood-to-plasma ratio of acalabrutinib and its active metabolite, ACP-5862, was 0.8 and 0.7, respectively.

Elimination

The geometric mean (% CV) terminal elimination half-life (t1/2) of acalabrutinib and its active metabolite, ACP-5862, were 1.4 (50%) hours and 6.4 (37%) hours, respectively. The geometric mean (%CV) apparent oral clearance (CL/F) of acalabrutinib and its active metabolite, ACP-5862, were 148 (33%) L/hr and 19 (23%) L/hr, respectively.

Metabolism

Acalabrutinib is predominantly metabolized by CYP3A enzymes, and to a minor extent, by glutathione conjugation and amide hydrolysis, based on in vitro studies. ACP-5862 was identified as the major active metabolite in plasma with a geometric mean exposure (AUC) that was approximately 2- to 3-fold higher than the exposure of acalabrutinib. ACP-5862 is approximately 50% less potent than acalabrutinib with regard to BTK inhibition.

Excretion

Following administration of a single 100 mg radiolabeled acalabrutinib dose in healthy subjects, 84% of the dose was recovered in the feces (< 2% unchanged) and 12% of the dose was recovered in the urine (< 2% unchanged).

Specific Populations

There were no clinically significant differences in the pharmacokinetics of acalabrutinib and its active metabolite, ACP‑5862, based on age (32 to 90 years), sex, race (Caucasian, African American), body weight (40 to 149 kg), or mild to moderate renal impairment (estimated glomerular filtration rate [eGFR] by Modification of Diet in Renal Disease [MDRD] equation: 30 to < 90 mL/min). The effect of severe renal impairment (eGFR < 30 mL/min, MDRD) or renal impairment requiring dialysis on the pharmacokinetics of acalabrutinib is unknown.

Patients with Hepatic Impairment

The AUC of acalabrutinib increased 1.9-fold in subjects with mild hepatic impairment (Child-Pugh class A), 1.5-fold in subjects with moderate hepatic impairment (Child-Pugh class B) and 5.3-fold in subjects with severe hepatic impairment (Child-Pugh class C) compared to subjects with normal liver function. No clinically relevant PK difference in ACP-5862 was observed in subjects with severe hepatic impairment (Child-Pugh Class C) compared to subjects with normal liver function. of acalabrutinib increased 1.9-fold in subjects with mild hepatic impairment (Child-Pugh class A), 1.5-fold in subjects with moderate hepatic impairment (Child-Pugh class B) and 5.3-fold in subjects with severe hepatic impairment (Child-Pugh class C) compared to subjects with normal liver function. No clinically relevant PK difference in ACP-5862 was observed in subjects with severe hepatic impairment (Child-Pugh Class C) compared to subjects with normal liver function. No clinically relevant PK differences in acalabrutinib and ACP-5862 were observed in patients with mild or moderate hepatic impairment (total bilirubin ≤ 3 x ULN and any AST) relative to patients with normal hepatic function (total bilirubin and AST ≤ ULN).

Drug Interaction Studies

Clinical Studies and Model-Informed Approaches

Strong CYP3A Inhibitors: Co-administration of acalabrutinib with itraconazole (strong CYP3A inhibitor) increase acalabrutinib Cmax by 3.9-fold and AUC by 5.1-fold in healthy subjects.

Moderate CYP3A Inhibitors: Co-administration of acalabrutinib with erythromycin (moderate CYP3A inhibitor), fluconazole (moderate CYP3A inhibitor), diltiazem (moderate CYP3A inhibitor) is predicted to increase acalabrutinib Cmax and AUC by approximately 2- to 3-fold.

Strong CYP3A Inducers: Co-administration of acalabrutinib with rifampin (strong CYP3A inducer) decreased acalabrutinib Cmax by 68% and AUC by 77% in healthy subjects.

Acid-Reducing Agents: No clinically significant differences in the pharmacokinetics of acalabrutinib were observed when co-administered with rabeprazole (proton pump inhibitor).

In Vitro Studies

Cytochrome P450 (CYP) Enzymes: Acalabrutinib is an inhibitor of CYP3A4/5, CYP2C8 and CYP2C9, but not CYP1A2, CYP2B6, CYP2C19, or CYP2D6. Acalabrutinib’s active metabolite, ACP-5862, is an inhibitor of CYP2C8, CYP2C9 and CYP2C19, but not CYP1A2, CYP2B6, CYP2D6, or CYP3A4/5. Acalabrutinib is an inducer of CYP1A2, CYP2B6, and CYP3A4. Acalabrutinib’s active metabolite, ACP-5862, is an inducer of CYP3A4.

Uridine diphosphate (UDP)-glucuronosyl transferase (UGT) Enzymes: Acalabrutinib and its active metabolite, ACP‑5862, are not inhibitors of UGT1A1 or UGT2B7.

Transporter System: Acalabrutinib is an inhibitor of breast cancer resistance protein (BCRP), but not multidrug and toxin extrusion protein 1 (MATE1). Acalabrutinib’s active metabolite, ACP-5862, is an inhibitor of MATE1, but not BCRP. Acalabrutinib and its active metabolite, ACP-5862, are not inhibitors of P-glycoprotein (P-gp), organic anion transporter (OAT) 1, OAT3, organic cation transporter 2 (OCT2), organic anion transporting polypeptide (OATP) 1B1, OATP1B3, or MATE2-K.

Acalabrutinib and its active metabolite, ACP-5862, are substrates of P-gp and BCRP. Acalabrutinib is not a substrate of OAT1, OAT3, OCT2, OATP1B1, or OATP1B3. Acalabrutinib’s active metabolite, ACP-5862, is not a substrate of OATP1B1 or OATP1B3.

13 NONCLINICAL TOXICOLOGY

13.1 Carcinogenesis, Mutagenesis, Impairment of Fertility

Carcinogenicity studies have not been conducted with acalabrutinib.

Acalabrutinib was not mutagenic in an in vitro bacterial reverse mutation (AMES) assay or clastogenic in an in vitro human lymphocyte chromosomal aberration assay or in an in vivo rat bone marrow micronucleus assay.

In a fertility study in rats, there were no effects of acalabrutinib on fertility in male rats at exposures 11 times, or in female rats at exposures 9 times, the AUC observed in patients at the recommended dose of 100 mg twice daily.

14 CLINICAL STUDIES

14.1 Previously Untreated Mantle Cell Lymphoma DOCVARIABLE vault_nd_4d1e0c80-2ff6-409f-bee7-897264eadbff \* MERGEFORMAT

ECHO

The efficacy of CALQUENCE in patients with previously untreated MCL was evaluated in a randomized, double blind, placebo controlled, multicenter study (ECHO; NCT02972840). The study enrolled 598 patients who were ≥ 65 years of age and who had no intention for transplant. The study excluded patients with total bilirubin > 1.5 × upper limit of normal (ULN), AST or ALT > 2.5 × ULN, or estimated creatinine clearance of ≤ 50 mL/min. Patients were randomized in a 1:1 ratio to receive CALQUENCE plus bendamustine and rituximab (CALQUENCE plus BR) or placebo plus BR. Dosing for both arms was administered in 28-day cycles as follows:

- CALQUENCE plus BR was administered for a maximum of 6 treatment cycles. CALQUENCE 100 mg orally was administered twice daily starting on Cycle 1 Day 1. Bendamustine was administered at 90 mg/m^2 intravenously over 30 minutes on Days 1 and 2 of each of 6 cycles. Rituximab was administered at 375 mg/m^2 intravenously on Day 1 of each cycle for 6 cycles.
- For patients achieving a response (PR or CR), CALQUENCE 100 mg orally twice daily was administered continuously, in combination with rituximab given at 375 mg/m^2 on Day 1 every other cycle for a maximum of 12 additional doses up to Cycle 30. After discontinuation of rituximab, patients continued CALQUENCE monotherapy at 100 mg orally twice daily until disease progression or unacceptable toxicity.

Patients on the control arm received the same regimen but placebo in lieu of CALQUENCE. Crossover to CALQUENCE monotherapy was permitted for patients in the placebo plus BR arm at disease progression.

Of all patients randomized, the median age was 71 years (range: 65-86); 71% were male; 78% were White, 16% Asian, 0.5% were Black or African American. In total, 80% had classic histology of MCL, 7.7% had blastoid MCL, and 5.5% had pleomorphic MCL. The simplified MIPI (Mantle Cell Lymphoma International Prognostic Index) score was low in 33%, intermediate in 43%, and high in 24% of patients. A total of 38% of patients had tumor bulk ≥ 5 cm and 86% had Ann Arbor stage IV disease.

The major efficacy outcome was progression-free survival (PFS) as assessed by an Independent Review Committee (IRC) using the Lugano Classification. Efficacy results are presented in Table 15. The Kaplan-Meier curves for PFS are shown in Figure 1. At this prespecified interim analysis, the median follow-up for PFS was 49.8 months in both arms.

Table 15. Efficacy Results in Patients with Previously Untreated MCL in ECHO
Outcomes per IRC | CALQUENCE plus BR; N= 299 | Placebo plus BR; N= 299
Progression-Free Survivala
Median (95% CI), months | 66.4 (55.1, NE) | 49.6 (36.0, 64.1)
HRb (95% CI) | 0.73 (0.57, 0.94)
P-valuec | 0.016
Overall Response Rate (ORR) (CR + PR)
ORR n (%) | 272 (91) | 263 (88)
95% CI | 87, 94 | 84, 91
CR n (%) | 199 (67) | 160 (54)
PR n (%) | 73 (24) | 103 (34)
p-value | 0.220
HR = hazard ratio, CR = complete response, PR = partial response, NE – not evaluable

a Stratified by randomization stratification factors: Geographic Regions (North American, Western Europe, Other) and simplified MIPI Score (Low risk [0 to 3], Intermediate risk [4 to 5], High Risk [6 to 11]).

b Estimated based on stratified Cox Proportional Hazards model for hazard ratio (95% CI).

c Estimated based on stratified log-rank test for p-value, with an alpha level of 0.039 derived by the O’Brien-Fleming method.

Figure 1. Kaplan-Meier Curve of IRC-Assessed PFS in Patients with Previously Untreated MCL in ECHO

At the time of the PFS analysis, the median overall survival had not been reached in either arm with a total of 203 deaths: 97 (32%) patients in the CALQUENCE plus BR arm and 106 (35%) patients in the placebo plus BR arm had died.

14.2 Previously Treated Mantle Cell Lymphoma

ACE-LY-004

The efficacy of CALQUENCE was based upon Trial LY-004 titled “An Open-label, Phase 2 Study of ACP-196 in Subjects with Mantle Cell Lymphoma” (NCT02213926). Trial LY-004 enrolled a total of 124 patients with MCL who had received at least one prior therapy.

The median age was 68 (range 42 to 90) years, 80% were male, and 74% were Caucasian. At baseline, 93% of patients had an ECOG performance status of 0 or 1. The median time since diagnosis was 46.3 months and the median number of prior treatments was 2 (range 1 to 5), including 18% with prior stem cell transplant. Patients who received prior treatment with BTK inhibitors were excluded. The most common prior regimens were CHOP-based (52%) and ARA-C (34%). At baseline, 37% of patients had at least one tumor with a longest diameter ≥ 5 cm, 73% had extra nodal involvement including 51% with bone marrow involvement. The simplified Mantle Cell Lymphoma International Prognostic Index (MIPI) score (which includes age, ECOG score, and baseline lactate dehydrogenase and white cell count) was intermediate in 44% and high in 17% of patients.

CALQUENCE was administered orally at 100 mg approximately every 12 hours until disease progression or unacceptable toxicity. The median dose intensity was 98.5%. The major efficacy outcome of Trial LY-004 was overall response rate and the median follow-up was 15.2 months.

Table 16: Efficacy Results in Patients with MCL in Trial LY-004
 | Investigator Assessed; N=124 | Independent Review Committee (IRC) Assessed; N=124
Overall Response Rate (ORR) [Per 2014 Lugano Classification.]
ORR (%) [95% CI] | 81 [73, 87] | 80 [72, 87]
Complete Response (%) [95% CI] | 40 [31, 49] | 40 [31, 49]
Partial Response (%) [95% CI] | 41 [32, 50] | 40 [32, 50]
Duration of Response (DoR)
Median DoR in months [range] | NE [1+ to 20+] | NE [0+ to 20+]
CI= Confidence Interval; NE=Not Estimable; + indicates censored observations.

The median time to best response was 1.9 months.

Lymphocytosis

Upon initiation of CALQUENCE, a temporary increase in lymphocyte counts (defined as absolute lymphocyte count increased ≥ 50% from baseline and a post-baseline assessment ≥ 5 x 109/L) in 31.5% of patients in Trial LY-004. The median time to onset of lymphocytosis was 1.1 weeks, and the median duration of lymphocytosis was 6.7 weeks.

14.3 Chronic Lymphocytic Leukemia

The efficacy of CALQUENCE in patients with CLL was demonstrated in two randomized, controlled trials. The indication for CALQUENCE includes patients with SLL because it is the same disease.

ELEVATE-TN

The efficacy of CALQUENCE was evaluated in the ELEVATE-TN trial, a randomized, multicenter, open-label, actively controlled, 3 arm trial of CALQUENCE in combination with obinutuzumab, CALQUENCE monotherapy, and obinutuzumab in combination with chlorambucil in 535 patients with previously untreated chronic lymphocytic leukemia (NCT02475681). Patients 65 years of age or older or between 18 and 65 years of age with a total Cumulative Illness Rating Scale (CIRS) > 6 or creatinine clearance of 30 to 69 mL/min were enrolled. The trial also required hepatic transaminases ≤ 3 times upper limit of normal (ULN) and total bilirubin ≤ 1.5 times ULN, and excluded patients with Richter’s transformation.

Patients were randomized in a 1:1:1 ratio into 3 arms to receive:

- CALQUENCE plus obinutuzumab (CALQUENCE+G): CALQUENCE 100 mg was administered approximately every 12 hours starting on Cycle 1 Day 1 until disease progression or unacceptable toxicity. Obinutuzumab was administered starting on Cycle 2 Day 1 for a maximum of 6 treatment cycles. Obinutuzumab 1,000 mg was administered on Days 1 and 2 (100 mg on Day 1 and 900 mg on Day 2), 8 and 15 of Cycle 2 followed by 1,000 mg on Day 1 of Cycles 3 up to 7. Each cycle was 28 days.
- CALQUENCE monotherapy: CALQUENCE 100 mg was administered approximately every 12 hours until disease progression or unacceptable toxicity.
- Obinutuzumab plus chlorambucil (GClb): Obinutuzumab and chlorambucil were administered for a maximum of 6 treatment cycles. Obinutuzumab 1,000 mg was administered intravenously on Days 1 and 2 (100 mg on Day 1 and 900 mg on Day 2), 8 and 15 of Cycle 1 followed by 1,000 mg on Day 1 of Cycles 2 to 6. Chlorambucil 0.5 mg/kg was administered orally on Days 1 and 15 of Cycles 1 to 6. Each cycle was 28 days.

Randomization was stratified by 17p deletion mutation status, ECOG performance status (0 or 1 versus 2), and geographic region. A total of 535 patients were randomized, 179 to CALQUENCE+G, 179 to CALQUENCE monotherapy, and 177 to GClb. The overall median age was 70 years (range: 41 to 91 years), 47% had Rai stage III or IV disease, 14% had 17p deletion or TP53 mutation, 63% of patients had an unmutated IGVH, and 18% had 11q deletion. Baseline demographic and disease characteristics were similar between treatment arms.

Efficacy was based on progression-free survival (PFS) as assessed by an Independent Review Committee (IRC). The median duration of follow-up was 28.3 months (range: 0.0 to 40.8 months). Efficacy results are presented in Table 17. The Kaplan-Meier curves for PFS are shown in Figure 2.

Table 17. Efficacy Results per IRC in Patients with CLL ‒ ITT population (ELEVATE-TN)
 | CALQUENCE plus Obinutuzumab; N=179 | CALQUENCE Monotherapy; N=179 | Obinutuzumab plus Chlorambucil; N=177
Progression-Free Survival [Per 2008 International Workshop on CLL (IWCLL) criteria.]
Number of events (%) | 14 (8) | 26 (15) | 93 (53)
PD, n (%) | 9 (5) | 20 (11) | 82 (46)
Death events, n (%) | 5 (3) | 6 (3) | 11 (6)
Median (95% CI), months [Kaplan-Meier estimate.] | NE | NE (34, NE) | 22.6 (20, 28)
HR [Based on a stratified Cox-Proportional-Hazards model. Both hazard ratios are compared with the obinutuzumab and chlorambucil arm.] (95% CI) | 0.10 (0.06, 0.17) | 0.20 (0.13, 0.30) | -
p-value [Based on a stratified log-rank test, with an alpha level of 0.012 derived from alpha spending function by the O’Brien-Fleming method.] | < 0.0001 | < 0.0001 | -
Overall Response Rate (CR + CRi + nPR + PR)
ORR, n (%) | 168 (94) | 153 (86) | 139 (79)
(95% CI) | (89, 97) | (80, 90) | (72, 84)
p-value [Based on a stratified Cochran–Mantel–Haenszel test, for the comparison with the obinutuzumab and chlorambucil arm.] | < 0.0001 | 0.0763 | -
CR, n (%) | 23 (13) | 1 (1) | 8 (5)
CRi, n (%) | 1 (1) | 0 | 0
nPR, n (%) | 1 (1) | 2 (1) | 3 (2)
PR, n (%) | 143 (80) | 150 (84) | 128 (72)
ITT=intent-to-treat; CI=confidence interval; HR=hazard ratio; NE=not estimable; CR=complete response; CRi=complete response with incomplete blood count recovery; nPR=nodular partial response; PR=partial response.

Figure 2: Kaplan-Meier Curve of IRC-Assessed PFS in Patients with CLL in ELEVATE-TN

With a median follow-up of 28.3 months, median overall survival was not reached in any arm, with fewer than 10% of patients experiencing an event.

ASCEND

The efficacy of CALQUENCE in patients with relapsed or refractory CLL was based upon a multicenter, randomized, open-label trial (ASCEND; NCT02970318). The trial enrolled 310 patients with relapsed or refractory CLL after at least 1 prior systemic therapy. The trial excluded patients with transformed disease, prolymphocytic leukemia, or previous treatment with venetoclax, a Bruton tyrosine kinase inhibitor, or a phosphoinositide-3 kinase inhibitor.

Patients were randomized in a 1:1 ratio to receive either:

- CALQUENCE 100 mg approximately every 12 hours until disease progression or unacceptable toxicity, or
- Investigator’s choice:
  ∘ Idelalisib plus a rituximab product (IR): Idelalisib 150 mg orally approximately every 12 hours until disease progression or unacceptable toxicity, in combination with 8 infusions of a rituximab product (375 mg/m^2 intravenously on Day 1 of Cycle 1, followed by 500 mg/m^2 every 2 weeks for 4 doses and then every 4 weeks for 3 doses), with a 28-day cycle length.
  ∘ Bendamustine plus a rituximab product (BR): Bendamustine 70 mg/m^2 intravenously (Day 1 and 2 of each 28-day cycle), in combination with a rituximab product (375 mg/m2 intravenously on Day 1 of Cycle 1, then 500 mg/m^2 on Day 1 of subsequent cycles), for up to 6 cycles.

Randomization was stratified by 17p deletion mutation status, ECOG performance status (0 or 1 versus 2), and number of prior therapies (1 to 3 versus ≥ 4). Of 310 patients total, 155 were assigned to CALQUENCE monotherapy, 119 to IR, and 36 to BR. The median age overall was 67 years (range: 32 to 90 years), 42% had Rai stage III or IV disease, 28% had 17p deletion or TP53 mutation, 78% of patients had an unmutated IGVH, and 27% had a 11q deletion. The CALQUENCE arm had a median of 1 prior therapy (range: 1 to 8), with 47% having at least 2 prior therapies. The investigator’s choice arm had a median of 2 prior therapies (range: 1 to 10), with 57% having at least 2 prior therapies.

In the CALQUENCE arm, the median treatment duration was 15.7 months, with 94% of patients treated for at least 6 months and 86% of patients treated for at least 1 year. In the investigator’s choice arm, the median treatment duration was 8.4 months, with 59% of patients treated for at least 6 months and 37% treated for at least 1 year.

Efficacy was based on PFS as assessed by an IRC, with a median follow-up of 16.1 months (range 0.03 to 22.4 months). Efficacy results are presented in Table 18. The Kaplan-Meier curve for PFS is shown in Figure 3. There was no statistically significant difference in overall response rates between the two treatment arms.

Table 18: Efficacy Results per IRC in Patients with Relapsed or Refractory CLL – ITT Population (ASCEND)
 | CALQUENCE Monotherapy; N=155 | Investigator’s Choice of Idelalisib + Rituximab Product or Bendamustine + Rituximab Product; N=155
Progression-Free Survival [Per 2008 IWCLL criteria.]
Number of events, n (%) | 27 (17) | 68 (44)
Disease progression, n | 19 | 59
Death, n | 8 | 9
Median (95% CI), months [Kaplan-Meier estimate.] | NE (NE, NE) | 16.5 (14.0, 17.1)
HR (95% CI) [Based on a stratified Cox-Proportional-Hazards model.] | 0.31 (0.20, 0.49)
P-value [Based on a stratified Log-rank test. The pre-specified type I error rate (α) for this interim analysis is 0.012 derived from a Lan-DeMets alpha spending function with O’Brien-Fleming boundary.] | < 0.0001
Overall Response Rate (CR + CRi + nPR + PR) [Through a hierarchical testing procedure, the difference in ORR was not statistically significant, based on a Cochran-Mantel-Haenszel test with adjustment for randomization stratification factors.]
ORR, n (%) | 126 (81) | 117 (75)
(95% CI) | (74, 87) | (68, 82)
CR, n (%) | 0 | 2 (1)
CRi, n (%) | 0 | 0
nPR, n (%) | 0 | 0
PR, n (%) | 126 (81) | 115 (74)
ITT=intent-to-treat; CI=confidence interval; HR=hazard ratio; NE=not estimable; CR=complete response; CRi=complete response with incomplete blood count recovery; nPR=nodular partial response; PR=partial response

Figure 3: Kaplan-Meier Curve of IRC-Assessed PFS in Patients with CLL in ASCEND

With a median follow-up of 16.1 months, median overall survival was not reached in either arm, with fewer than 11% of patients experiencing an event.

AMPLIFY

The efficacy of CALQUENCE in combination with venetoclax in previously untreated CLL patients was evaluated in AMPLIFY, a randomized, multi-center, open-label study (NCT03836261). The study included patients previously untreated for CLL without del(17p) or TP53 mutation that were 18 years of age and older. Patients were randomized to receive:

- CALQUENCE plus venetoclax (AV): CALQUENCE 100 mg was administered twice daily starting on Cycle 1 Day 1 for a total of 14 cycles or until disease progression or unacceptable toxicity. On Cycle 3 Day 1 patients started the venetoclax 5-week dose-titration schedule, starting at 20 mg and increasing weekly to 50 mg, 100 mg, 200 mg and finally 400 mg once daily. Venetoclax was administered for a total of 12 cycles. Each cycle was 28 days.
- Investigator’s choice of chemoimmunotherapy (FCR/BR):
  - Fludarabine plus cyclophosphamide plus rituximab (FCR): Fludarabine (25 mg/m2) and cyclophosphamide (250 mg/m^2) were administered on Days 1–3 up to a maximum of 6 cycles. Rituximab was administered at a dose of 375 mg/m^2 on Day 1 Cycle 1 and 500 mg/m2 on Day 1 of Cycles 2 up to 6. Each cycle was 28 days.
  - Bendamustine plus rituximab (BR): Bendamustine 90 mg/m2 was administered on Days 1 and 2 up to maximum of 6 cycles. Rituximab was administered at a dose of 375 mg/m2 on Day 1 Cycle 1 and 500 mg/m2 on Day 1 of Cycles 2 up to 6. Each cycle was 28 days.
- An additional investigational combination regimen [see Warnings and Precautions (5.1)].

Patients were stratified by age (> 65 years or ≤ 65), IGHV mutational status (mutated versus unmutated), Rai stage (high risk [≥ 3] versus non-high risk) and geographic region (North America and Europe versus other). In the efficacy population described in Table 19, overall median age was 61 years (range: 26 to 86 years) and 62% were males; 89% were White, 3.8% Asian, 1.7% were Black or African American, 0.3% American Indian or Alaska Native, 0.3% Native Hawaiian or Other Pacific Islander, and 4.8% not reported; 86% were not Hispanic or Latino, 7% Hispanic or Latino, and 7% not reported. The ECOG performance was 0-1 in 90%, bulky diseases with nodes ≥ 5 cm was seen in 41%, 45% had Rai stage III or IV disease, 17% had 11q deletion and 58% had unmutated IGHV.

The major efficacy outcome was IRC-assessed PFS of AV arm versus Investigator’s choice arm (FCR/BR). The median duration of PFS follow-up was 42.6 months. Efficacy results are presented in Table 19. The Kaplan-Meier curve for IRC-assessed PFS is shown in Figure 4.

Table 19. Efficacy Results per IRC in Patients with previously untreated CLL ‒ ITT population (AMPLIFY)
 | CALQUENCE plus venetoclax; N=291 | FCR/BRb; N=290
Progression-free survivala
Number of events (%) | 89 (31) | 95 (33)
PD, n (%) | 77 (26) | 66 (23)
Death events (%) | 12 (4) | 29 (10)
Median (95% CI), months | NE (51.1, NE) | 47.6 (43.3, NE)
HRc (95% CI) | 0.65 (0.49, 0.87)
P-valued | 0.0038
Overall Response Rate (CR, CRi, nPR, PR)e
ORR n (%) | 270 (93) | 218 (75)
(95% CI) | (89, 95) | (70, 80)
CR | 26 (9) | 15 (5)
CRi, n (%) | 0 | 1 (0.3)
nPR, n (%) | 1 (0.3) | 1 (0.3)
PR n (%) | 243 (84) | 201 (69)
NE= Not estimable; CR = complete response; CRi=complete response with incomplete blood count recovery; nPR=nodular partial response; PR=partial response
a Per IRC assessment.
b Approximately 50% of patients were treated with FCR and 50% were treated with BR per investigator's choice.
c Based on stratified Cox-Proportional-Hazards model.
d Based on a stratified Log-rank test. The pre-specified type I error rate (α) for this interim analysis is 0.0469 derived from a Lan-DeMets alpha spending function with O’Brien-Fleming boundary.
e Per iwCLL 2018 criteria.

Figure 4: Kaplan-Meier Curve of IRC-Assessed PFS in Patients with previously untreated CLL in AMPLIFY

With a median follow-up of 41.0 months, a total of 60 death events were reported; 18 (6%) in the AV arm and 42 (14%) in the FCR/BR arm.

16 HOW SUPPLIED/STORAGE AND HANDLING

How Supplied

Pack Size | Contents | NDC Number
60-count bottle | Bottle containing 60 tablets with a child-resistant closure; 100 mg, orange, oval, biconvex tablet, with debossment ‘ACA100’ on one side and plain on the reverse | 0310-3512-60

Storage

Store at 20°C-25°C (68°F-77°F); excursions permitted to 15°C-30°C (59°F-86°F) [see USP Controlled Room Temperature].

17 PATIENT COUNSELING INFORMATION

Advise the patient to read the FDA-approved patient labeling (Patient Information).

Serious and Opportunistic Infections

Inform patients of the possibility of serious infection and to immediately report signs or symptoms suggestive of infection [see Warnings and Precautions (5.1)].

Hemorrhage

Inform patients to immediately report signs or symptoms of bleeding. Inform patients that CALQUENCE may need to be interrupted for major surgeries [see Warnings and Precautions (5.2)].

Cytopenias

Inform patients that they will need periodic blood tests to check blood counts during treatment with CALQUENCE [see Warnings and Precautions (5.3)].

Second Primary Malignancies

Inform patients that other malignancies have been reported in patients who have been treated with CALQUENCE, including skin cancer and other solid tumors. Advise patients to use sun protection [see Warnings and Precautions (5.4)].

Cardiac Arrhythmias

Counsel patients to immediately report any signs of palpitations, dizziness, fainting, chest discomfort, and shortness of breath [see Warnings and Precautions (5.5)].

Hepatotoxicity, Including Drug-Induced Liver Injury:

Inform patients that liver problems, including drug-induced liver injury and abnormalities in liver tests, may develop during CALQUENCE treatment. Advise patients to contact their healthcare provider immediately if they experience abdominal discomfort, dark urine, or jaundice [see Warnings and Precautions (5.6)].

Pregnancy Complication

CALQUENCE may cause fetal harm and dystocia. Advise women to use effective contraception during treatment and for 1 week after the last dose of CALQUENCE [see Use in Specific Populations (8.3)].

Lactation

Advise females not to breastfeed during treatment with CALQUENCE and for 2 weeks after the last dose [see Use in Specific Populations (8.2)].

Dosing Instructions

Instruct patients to take CALQUENCE orally twice daily, about 12 hours apart. CALQUENCE may be taken with or without food. Advise patients that CALQUENCE tablets should be swallowed whole with a glass of water, without chewing, crushing, dissolving, or cutting [see Dosage and Administration (2.1)].

Missed Dose

Advise patients that if they miss a dose of CALQUENCE, they may still take it up to 3 hours after the time they would normally take it. If more than 3 hours have elapsed, they should be instructed to skip that dose and take their next dose of CALQUENCE at the usual time. Warn patients they should not take extra tablets to make up for the dose that they missed [see Dosage and Administration (2.1)].

Drug Interactions

Advise patients to inform their healthcare providers of all concomitant medications, including over‑the‑counter medications, vitamins and herbal products [see Drug Interactions (7)].

Distributed by:

AstraZeneca Pharmaceuticals LP

Wilmington, DE 19850

CALQUENCE is a registered trademark of the AstraZeneca group of companies. ©AstraZeneca 2026

PATIENT INFORMATION

CALQUENCE® (KAL-kwens)
(acalabrutinib)
tablets

What is CALQUENCE?

CALQUENCE is a prescription medicine used to treat adults with:

- Mantle cell lymphoma (MCL) in combination with bendamustine and rituximab in people who have not had prior treatment for MCL and who cannot receive a type of stem cell transplant that uses their own blood stem cells (autologous hematopoietic stem cell transplantation).
- Mantle cell lymphoma (MCL) who have received at least one prior therapy.
- Chronic lymphocytic leukemia (CLL) or small lymphocytic lymphoma (SLL).

It is not known if CALQUENCE is safe and effective in children.

Before taking CALQUENCE, tell your healthcare provider about all of your medical conditions, including if you:

- have had recent surgery or plan to have surgery. Your healthcare provider may stop CALQUENCE for any planned medical, surgical, or dental procedure.
- have bleeding problems.
- have or had heart rhythm problems.
- have an infection.
- have or had liver problems, including hepatitis B virus (HBV) infection.
- are pregnant or plan to become pregnant. CALQUENCE may harm your unborn baby and cause problems during childbirth (dystocia).

Females who are able to become pregnant:

  ∘ Your healthcare provider may do a pregnancy test before you start treatment with CALQUENCE.
  ∘ Use effective birth control (contraception) during treatment with CALQUENCE and for 1 week after the last dose of CALQUENCE.
- are breastfeeding or plan to breastfeed. It is not known if CALQUENCE passes into your breast milk. Do not breastfeed during treatment with CALQUENCE and for 2 weeks after your last dose of CALQUENCE.

Tell your healthcare provider about all the medicines you take, including prescription and over-the-counter medicines, vitamins, and herbal supplements. Taking CALQUENCE with certain other medications may affect how CALQUENCE works and can cause side effects. Especially tell your healthcare provider if you take a blood thinner medicine.

How should I take CALQUENCE?

- Take CALQUENCE exactly as your healthcare provider tells you to take it.
- Do not change your dose or stop taking CALQUENCE unless your healthcare provider tells you to.
- Your healthcare provider may tell you to decrease your dose, temporarily stop, or completely stop taking CALQUENCE if you develop certain side effects.
- Do not switch (interchange) your CALQUENCE tablets with CALQUENCE capsules.
- Take CALQUENCE 2 times a day (about 12 hours apart).
- Take CALQUENCE with or without food.
- Swallow CALQUENCE tablets whole with a glass of water. Do not chew, crush, dissolve, or cut tablets.
- If you miss a dose of CALQUENCE, take it as soon as you remember. If it is more than 3 hours past your usual dosing time, skip the missed dose and take your next dose of CALQUENCE at your regularly scheduled time. Do not take an extra dose to make up for a missed dose.

What are the possible side effects of CALQUENCE?

CALQUENCE can cause serious side effects, including:

- Serious infections have happened in people treated with CALQUENCE and may lead to death. Your healthcare provider may prescribe certain medicines if you have an increased risk of getting infections. Tell your healthcare provider right away if you have any signs or symptoms of an infection, including fever, chills, or flu-like symptoms.
- Bleeding problems (hemorrhage) have happened in people treated with CALQUENCE and can be serious and may lead to death. Your risk of bleeding may increase if you are also taking a blood thinner medicine. Tell your healthcare provider right away if you have any signs or symptoms of bleeding, including:

  ∘ blood in your stools or black stools (looks like tar)
  ∘ pink or brown urine
  ∘ unexpected bleeding, or bleeding that is severe or you cannot control
  ∘ vomit blood or vomit that looks like coffee grounds
  ∘ cough up blood or blood clots

  ∘ dizziness
  ∘ weakness
  ∘ confusion
  ∘ changes in your speech
  ∘ headache that lasts a long time
  ∘ bruising or red or purple skin marks

- Decrease in blood cell counts. Decreased white blood cell counts, red blood cell counts, and platelet counts can be severe during treatment with CALQUENCE. Your healthcare provider should do blood tests to check your blood counts regularly during treatment with CALQUENCE.
- Second primary cancers. New cancers have happened in people during treatment with CALQUENCE, including cancers of the skin or other organs. Your healthcare provider will check you for skin cancers during treatment with CALQUENCE. Use sun protection when you are outside in sunlight.
- Heart rhythm problems (cardiac arrhythmias) have happened in people treated with CALQUENCE, and can be serious or lead to death. Tell your healthcare provider right away if you have any of the following signs or symptoms:

  ∘ fast or irregular heartbeat
  ∘ dizziness
  ∘ feeling faint

  ∘ chest discomfort
  ∘ shortness of breath

- Liver problems. Liver problems have happened in people treated with CALQUENCE, and can be severe or life-threatening, or lead to death. Tell your healthcare provider right away if you experience stomach pain or discomfort, urine of dark color or yellowing of your skin. Your healthcare provider will request tests to monitor your liver function during treatment with CALQUENCE.

The most common side effects of CALQUENCE include:

- upper respiratory infection
- diarrhea
- headache

- muscle and joint pain
- decreased white blood cell counts
- decreased platelet counts

These are not all of the possible side effects of CALQUENCE.

Call your doctor for medical advice about side effects. You may report side effects to FDA at 1-800-FDA-1088.

How should I store CALQUENCE?

- Store CALQUENCE at room temperature between 68°F to 77°F (20°C to 25°C).

Keep CALQUENCE and all medicines out of the reach of children.

General information about the safe and effective use of CALQUENCE.

Medicines are sometimes prescribed for purposes other than those listed in a Patient Information leaflet. Do not use CALQUENCE for a condition for which it was not prescribed. Do not give CALQUENCE to other people, even if they have the same symptoms you have. It may harm them. You can ask your healthcare provider or pharmacist for more information about CALQUENCE that is written for health professionals.

What are the ingredients in CALQUENCE?

Active ingredient: acalabrutinib

Inactive ingredients:

Tablet core: low-substituted hydroxypropyl cellulose, mannitol, microcrystalline cellulose, and sodium stearyl fumarate.

Tablet coating: copovidone, ferric oxide yellow, ferric oxide red, hypromellose, medium-chain triglycerides, polyethylene glycol 3350, purified water, and titanium dioxide.

Distributed by: AstraZeneca Pharmaceuticals LP, Wilmington, DE 19850

CALQUENCE is a registered trademark of the AstraZeneca group of companies. ©AstraZeneca 2026

For more information, go to www.CALQUENCE.com or call 1-800-236-9933.

This Patient Information has been approved by the U.S. Food and Drug Administration Revised: 2/2026

PACKAGE/LABEL PRINCIPAL DISPLAY PANEL

NDC 0310-3512-60

CALQUENCE®

(acalabrutinib) tablets

100 mg

Rx only

Do not chew, crush, dissolve, or cut tablets

Manufactured for:

AstraZeneca Pharmaceuticals LP

Wilmington, DE 19850

By: AstraZeneca AB

SE-151 85 Södertälje Sweden

Product of Switzerland

PACKAGE/LABEL PRINCIPAL DISPLAY PANEL

NDC 0310-4513-60

CALQUENCE®

(acalabrutinib) tablets

100 mg

Rx only

Do not chew, crush, dissolve, or cut

tablets

Manufactured for:

AstraZeneca Pharmaceuticals LP

Wilmington, DE 19850

AstraZeneca

60 tablets